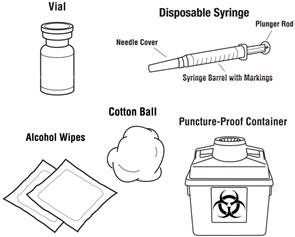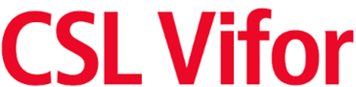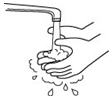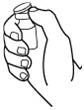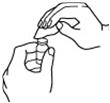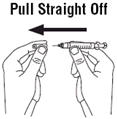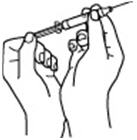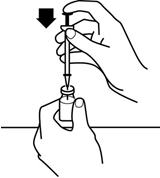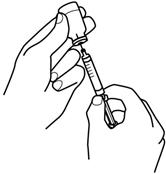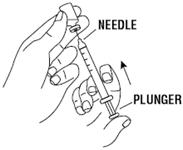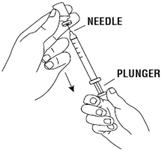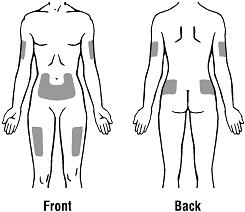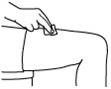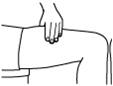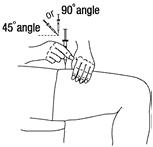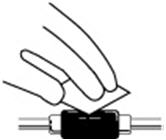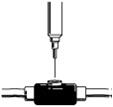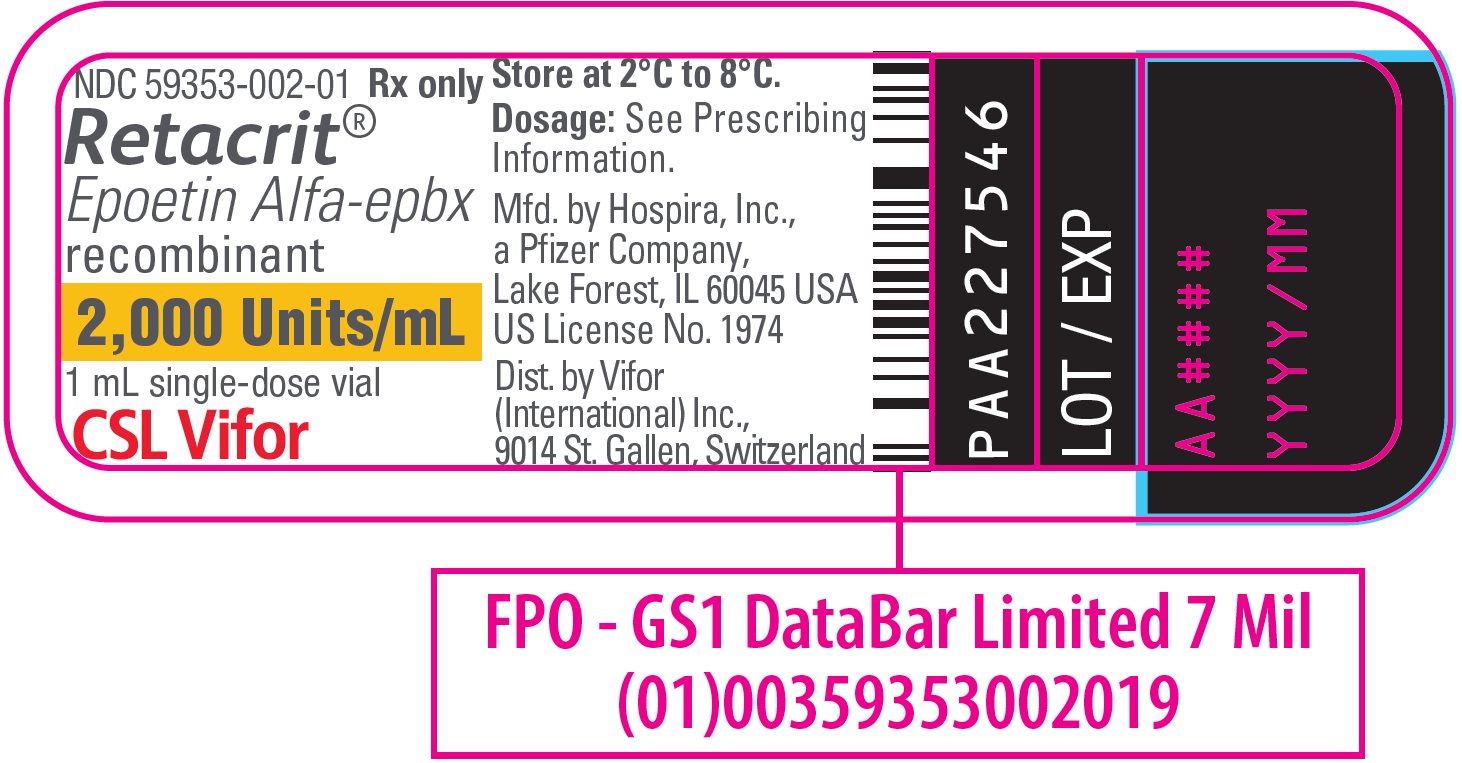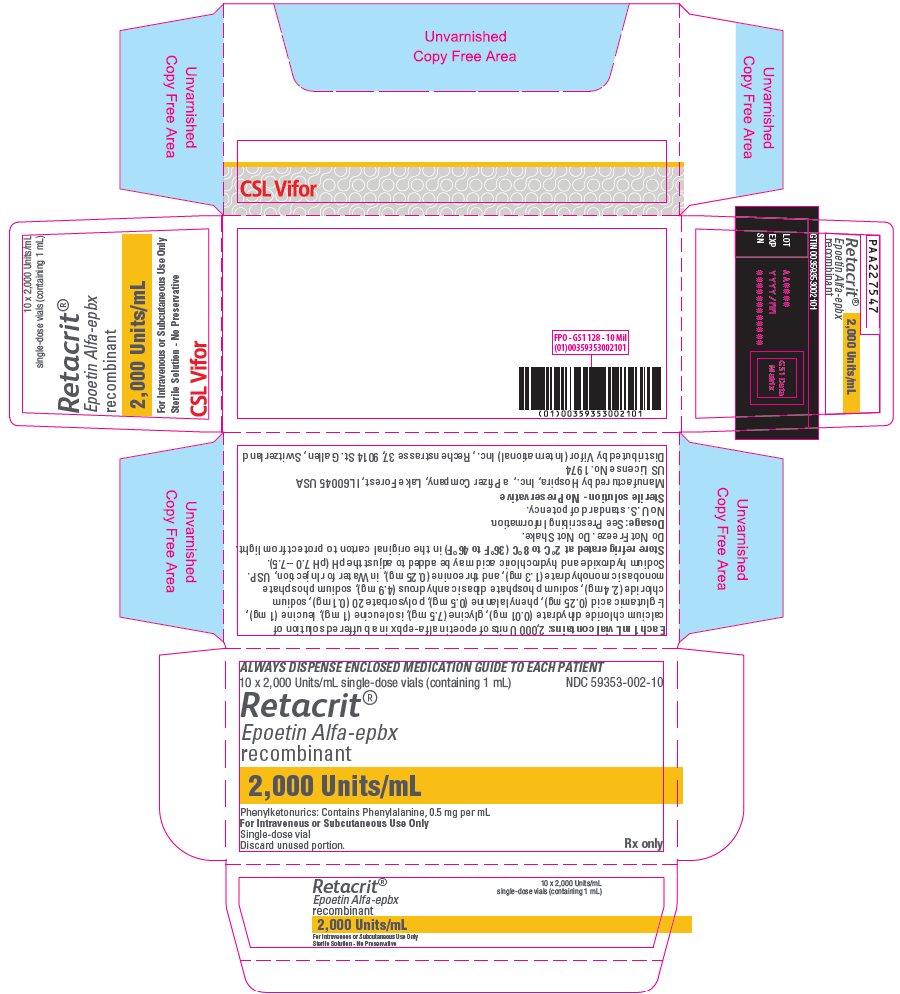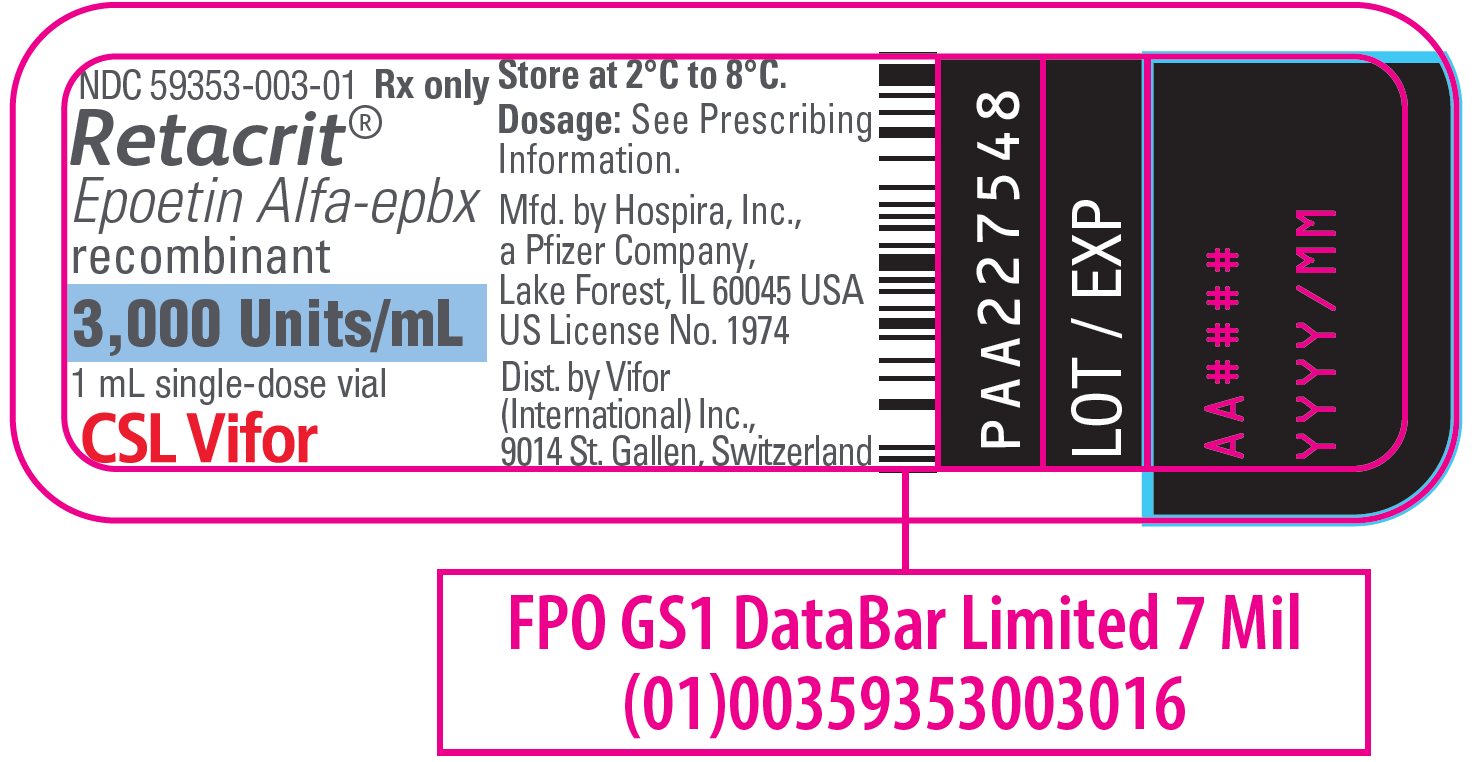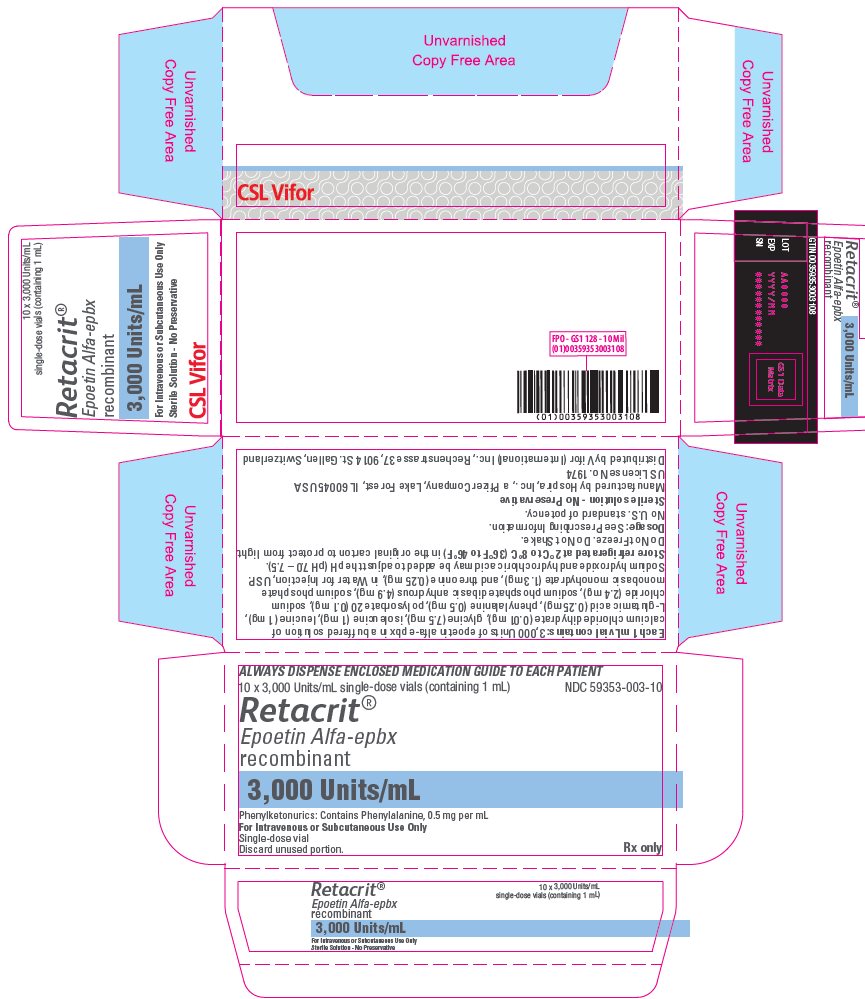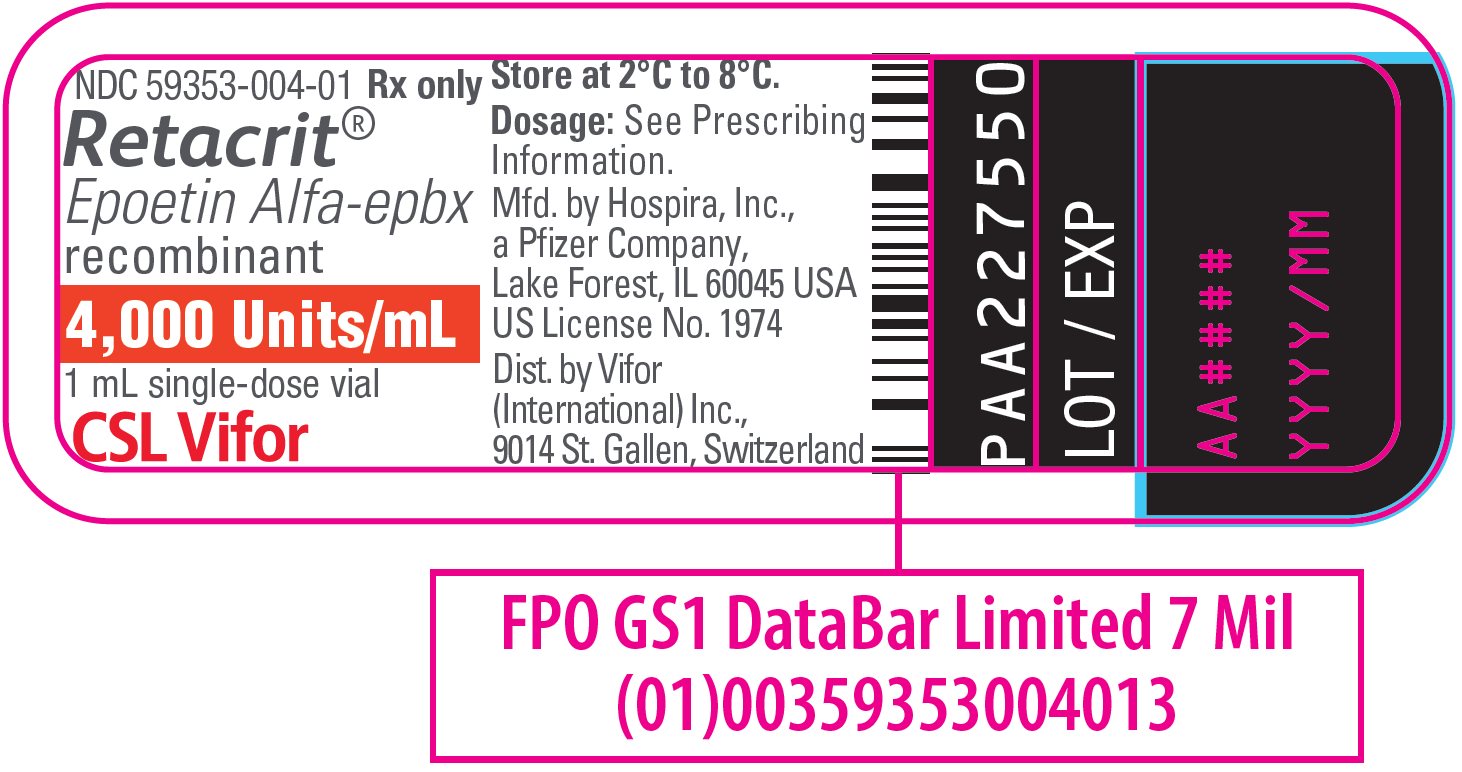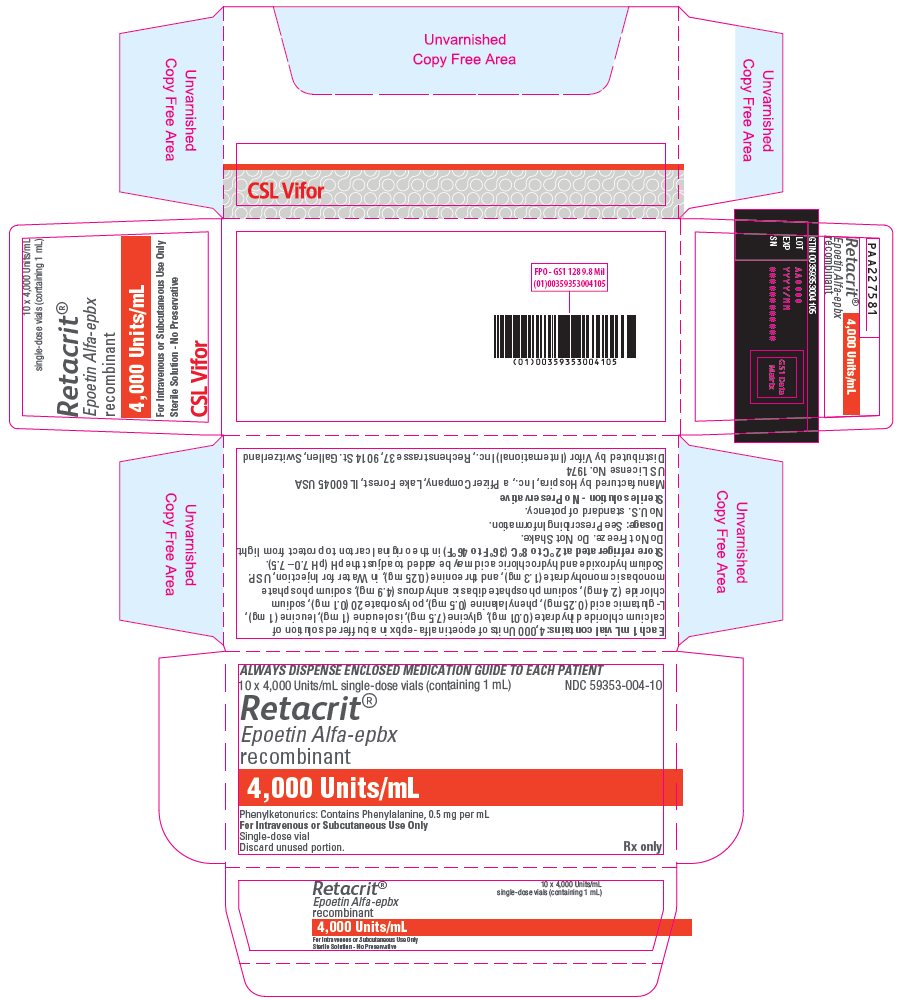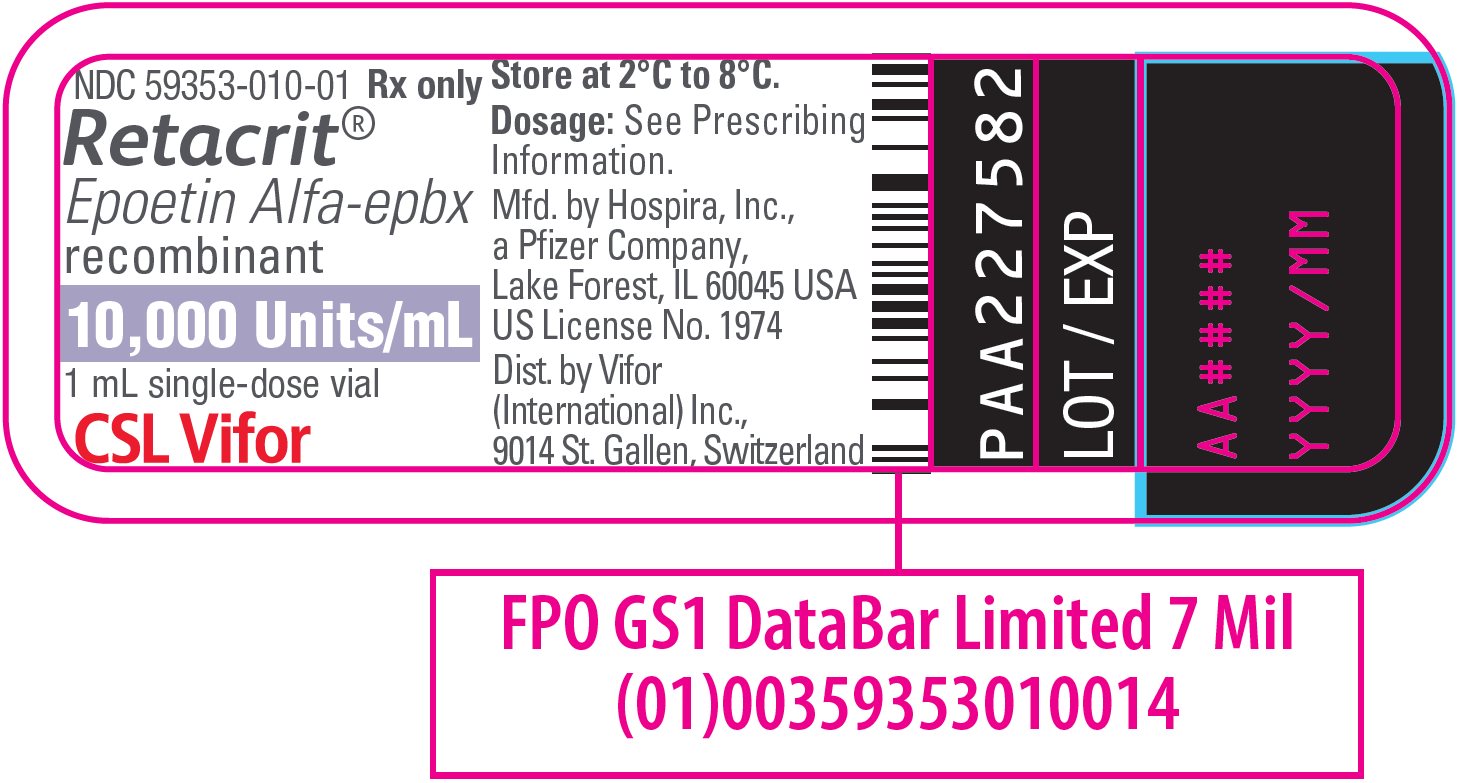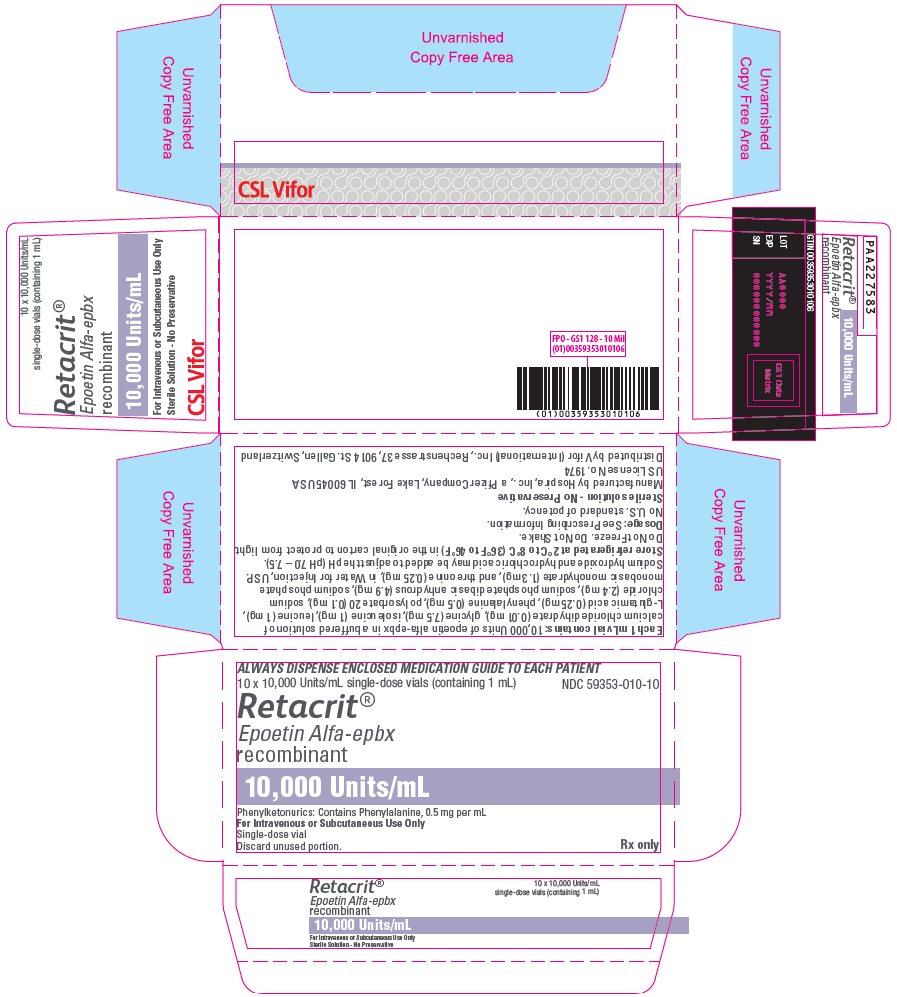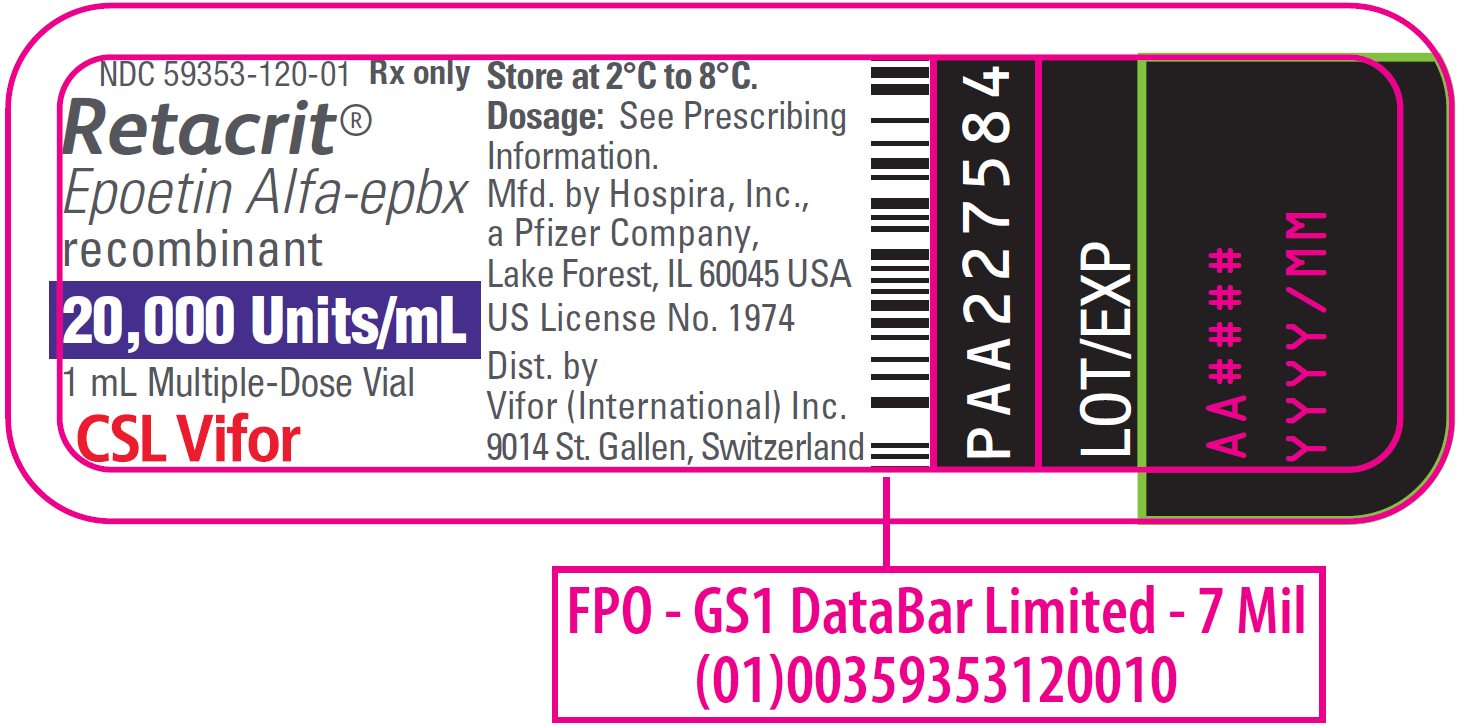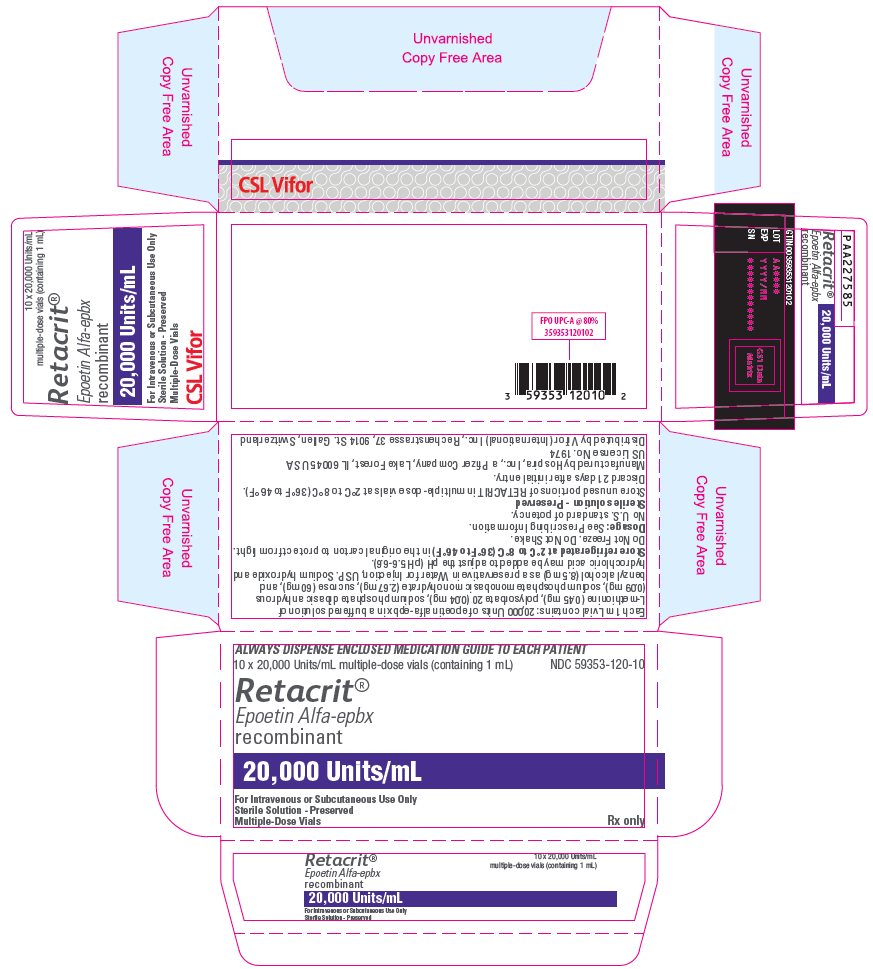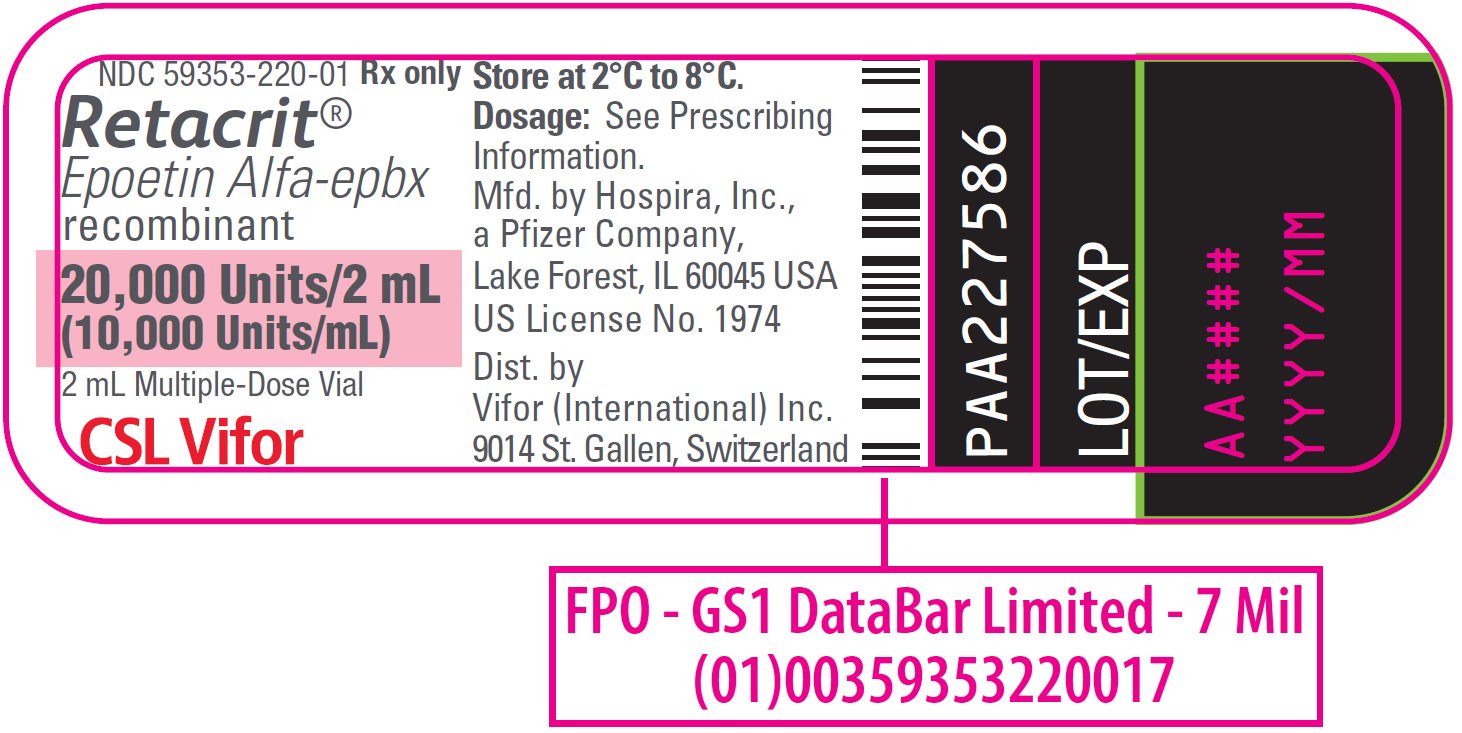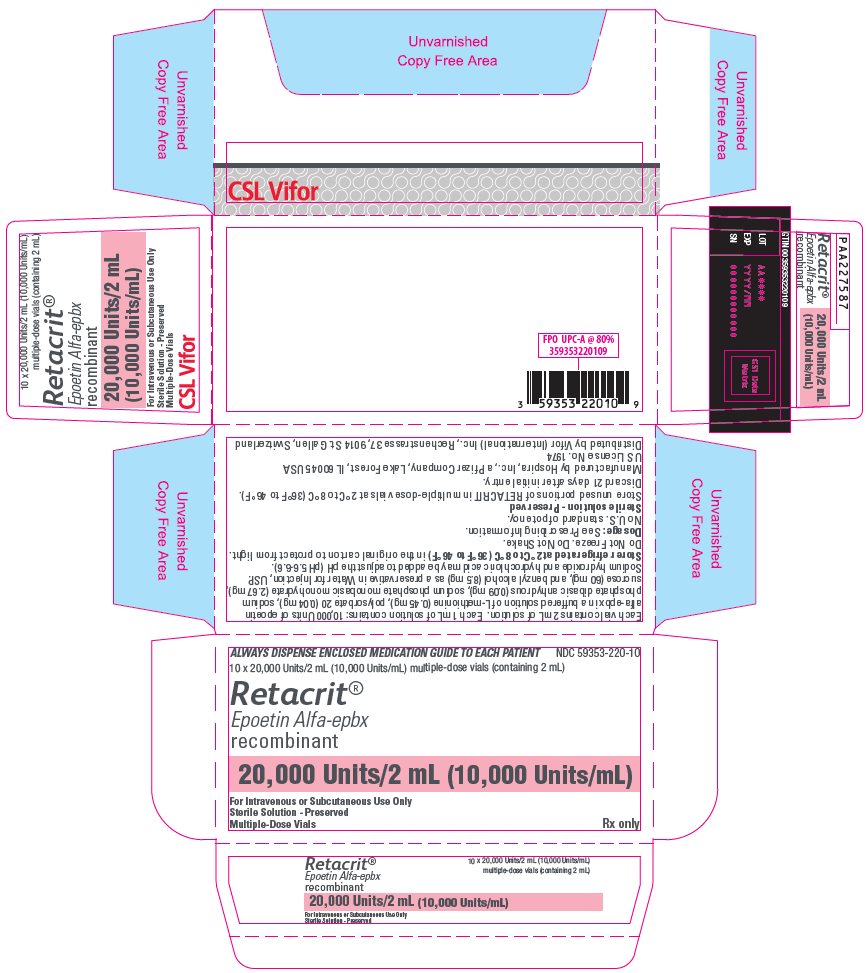 DRUG LABEL: RETACRIT
NDC: 59353-002 | Form: INJECTION, SOLUTION
Manufacturer: Vifor (International) Inc.
Category: prescription | Type: HUMAN PRESCRIPTION DRUG LABEL
Date: 20250622

ACTIVE INGREDIENTS: EPOETIN 2000 [iU]/1 mL
INACTIVE INGREDIENTS: SODIUM PHOSPHATE, MONOBASIC, MONOHYDRATE 1.3 mg/1 mL; SODIUM PHOSPHATE, DIBASIC, ANHYDROUS 4.9 mg/1 mL; SODIUM CHLORIDE 2.4 mg/1 mL; CALCIUM CHLORIDE 0.01 mg/1 mL; GLYCINE 7.5 mg/1 mL; LEUCINE 1 mg/1 mL; ISOLEUCINE 1 mg/1 mL; THREONINE 0.25 mg/1 mL; GLUTAMIC ACID 0.25 mg/1 mL; PHENYLALANINE 0.5 mg/1 mL; POLYSORBATE 20 0.1 mg/1 mL; WATER; SODIUM HYDROXIDE; HYDROCHLORIC ACID

HIGHLIGHTS OF PRESCRIBING INFORMATION

These highlights do not include all the information needed to use RETACRIT safely and effectively. See full prescribing information for RETACRIT.
RETACRIT® (epoetin alfa-epbx) injection, for intravenous or subcutaneous use
Initial U.S. Approval: 2018
RETACRIT (epoetin alfa-epbx) is biosimilar [Biosimilar means that the biological product is approved based on data demonstrating that it is highly similar to an FDA-approved biological product, known as a reference product, and that there are no clinically meaningful differences between the biosimilar product and the reference product. Biosimilarity of RETACRIT has been demonstrated for the condition(s) of use (e.g. indication(s), dosing regimen(s)), strength(s), dosage form(s), and route(s) of administration described in its Full Prescribing Information.] to EPOGEN/PROCRIT (epoetin alfa)

WARNING: ESAs INCREASE THE RISK OF DEATH, MYOCARDIAL INFARCTION, STROKE, VENOUS THROMBOEMBOLISM, THROMBOSIS OF VASCULAR ACCESS AND TUMOR PROGRESSION OR RECURRENCE

See full prescribing information for complete boxed warning.

Chronic Kidney Disease:

- In controlled trials, patients experienced greater risks for death, serious adverse cardiovascular reactions, and stroke when administered erythropoiesis-stimulating agents (ESAs) to target a hemoglobin level of greater than 11 g/dL (5.1).
- No trial has identified a hemoglobin target level, ESA dose, or dosing strategy that does not increase these risks (2.2).
- Use the lowest RETACRIT dose sufficient to reduce the need for red blood cell (RBC) transfusions (5.1).

Cancer:

- ESAs shortened overall survival and/or increased the risk of tumor progression or recurrence in clinical studies of patients with breast, non-small cell lung, head and neck, lymphoid, and cervical cancers (5.2).
- Use the lowest dose to avoid RBC transfusions (2.4).
- Use ESAs only for anemia from myelosuppressive chemotherapy (1.3).
- ESAs are not indicated for patients receiving myelosuppressive chemotherapy when the anticipated outcome is cure (1.5).
- Discontinue following the completion of a chemotherapy course (2.4).

Perisurgery:

- Due to increased risk of deep venous thrombosis (DVT), DVT prophylaxis is recommended (5.1).

1 INDICATIONS AND USAGE

RETACRIT is an erythropoiesis-stimulating agent (ESA) indicated for:

- Treatment of anemia due to
  - Chronic Kidney Disease (CKD) in patients on dialysis and not on dialysis (1.1).
  - Zidovudine in patients with Human Immunodeficiency Virus (HIV) infection (1.2).
  - The effects of concomitant myelosuppressive chemotherapy, and upon initiation, there is a minimum of two additional months of planned chemotherapy (1.3).
- Reduction of allogeneic red blood cell (RBC) transfusions in patients undergoing elective, noncardiac, nonvascular surgery (1.4).

Limitations of Use

RETACRIT has not been shown to improve quality of life, fatigue, or patient well-being (1.5).

RETACRIT is not indicated for use:

- In patients with cancer receiving hormonal agents, biologic products, or radiotherapy, unless also receiving concomitant myelosuppressive chemotherapy (1.5).
- In patients with cancer receiving myelosuppressive chemotherapy when the anticipated outcome is cure (1.5).
- In patients with cancer receiving myelosuppressive chemotherapy in whom the anemia can be managed by transfusion (1.5).
- In patients scheduled for surgery who are willing to donate autologous blood (1.5).
- In patients undergoing cardiac or vascular surgery (1.5).
- As a substitute for RBC transfusions in patients who require immediate correction of anemia (1.5).

2 DOSAGE AND ADMINISTRATION

- Evaluate iron status before and during treatment and maintain iron repletion. Correct or exclude other causes of anemia before initiating treatment (2.1).
- In pregnant women, lactating women, neonates, infants: Use only single-dose vials (2.1).
- Patients with CKD: Initial dose: 50 to 100 Units/kg 3 times weekly (adults) and 50 Units/kg 3 times weekly (pediatric patients). Individualize maintenance dose. Intravenous route recommended for patients on hemodialysis (2.2).
- Patients on Zidovudine due to HIV infection: 100 Units/kg 3 times weekly (2.3).
- Patients with Cancer on Chemotherapy: 40,000 Units weekly or 150 Units/kg 3 times weekly (adults); 600 Units/kg intravenously weekly (pediatric patients ≥ 5 years) (2.4).
- Surgery Patients: 300 Units/kg per day daily for 15 days or 600 Units/kg weekly (2.5).

3 DOSAGE FORMS AND STRENGTHS

Injection

- 2,000 Units/mL, 3,000 Units/mL, 4,000 Units/mL, and 10,000 Units/mL in single-dose vials (3).
- 20,000 Units/2 mL (10,000 Units/mL) and 20,000 Units/mL in multiple-dose vials containing benzyl alcohol (3).

4 CONTRAINDICATIONS

- Uncontrolled hypertension (4).
- Pure red cell aplasia (PRCA) that begins after treatment with RETACRIT or other erythropoietin protein drugs (4).
- Serious allergic reactions to RETACRIT or other epoetin alfa products (4).
- Use of the multiple-dose vials containing benzyl alcohol in neonates, infants, pregnant women, and lactating women (4).

5 WARNINGS AND PRECAUTIONS

- Increased Mortality, Myocardial Infarction, Stroke, and Thromboembolism: Using ESAs to target a hemoglobin level of greater than 11 g/dL increases the risk of serious adverse cardiovascular reactions and has not been shown to provide additional benefit (5.1 and 14.1). Use caution in patients with coexistent cardiovascular disease and stroke (5.1).
- Increased Mortality and/or Increased Risk of Tumor Progression or Recurrence in Patients with Cancer (5.2).
- Hypertension: Control hypertension prior to initiating and during treatment with RETACRIT (5.3).
- Seizures: Epoetin alfa products increase the risk for seizures in patients with CKD (5.4). Increase monitoring of these patients for changes in seizure frequency or premonitory symptoms (5.4).
- PRCA: If severe anemia and low reticulocyte count develop during RETACRIT treatment, withhold RETACRIT and evaluate for PRCA (5.6).
- Serious Allergic Reactions: Discontinue RETACRIT and manage reactions (5.7).
- Severe Cutaneous Reactions: Discontinue RETACRIT (5.8).
- Phenylketonurics: Contains phenylalanine (5.10).

6 ADVERSE REACTIONS

- Patients with CKD: Adverse reactions in ≥ 5% of epoetin alfa-treated patients in clinical studies were hypertension, arthralgia, muscle spasm, pyrexia, dizziness, medical device malfunction, vascular occlusion, and upper respiratory tract infection (6.1).
- Patients on Zidovudine due to HIV infection: Adverse reactions in ≥ 5% of epoetin alfa-treated patients in clinical studies were pyrexia, cough, rash, and injection site irritation (6.1).
- Patients with Cancer on Chemotherapy: Adverse reactions in ≥ 5% of epoetin alfa-treated patients in clinical studies were nausea, vomiting, myalgia, arthralgia, stomatitis, cough, weight decrease, leukopenia, bone pain, rash, hyperglycemia, insomnia, headache, depression, dysphagia, hypokalemia, and thrombosis (6.1).
- Surgery Patients: Adverse reactions in ≥ 5% of epoetin alfa-treated patients in clinical studies were nausea, vomiting, pruritus, headache, injection site pain, chills, deep vein thrombosis, cough, and hypertension (6.1).

To report SUSPECTED ADVERSE REACTIONS, contact Hospira, Inc., a Pfizer Company, at 1-800-438-1985, or FDA at 1-800-FDA-1088 or www.fda.gov/medwatch.

FULL PRESCRIBING INFORMATION

WARNING: ESAs INCREASE THE RISK OF DEATH, MYOCARDIAL INFARCTION, STROKE, VENOUS THROMBOEMBOLISM, THROMBOSIS OF VASCULAR ACCESS AND TUMOR PROGRESSION OR RECURRENCE

Chronic Kidney Disease:

- In controlled trials, patients with chronic kidney disease (CKD) experienced greater risks for death, serious adverse cardiovascular reactions, and stroke when administered erythropoiesis-stimulating agents (ESAs) to target a hemoglobin level of greater than 11 g/dL [see Warnings and Precautions (5.1)].
- No trial has identified a hemoglobin target level, ESA dose, or dosing strategy that does not increase these risks [see Dosage and Administration (2.2)].
- Use the lowest RETACRIT dose sufficient to reduce the need for red blood cell (RBC) transfusions [see Warnings and Precautions (5.1)].

Cancer:

- ESAs shortened overall survival and/or increased the risk of tumor progression or recurrence in clinical studies of patients with breast, non-small cell lung, head and neck, lymphoid, and cervical cancers [see Warnings and Precautions (5.2)].
- To decrease these risks, as well as the risk of serious cardiovascular and thromboembolic reactions, use the lowest dose needed to avoid RBC transfusions [see Dosage and Administration (2.4)].
- Use ESAs only for anemia from myelosuppressive chemotherapy [see Indications and Usage (1.3)].
- ESAs are not indicated for patients receiving myelosuppressive chemotherapy when the anticipated outcome is cure [see Indications and Usage (1.5)].
- Discontinue following the completion of a chemotherapy course [see Dosage and Administration (2.4)].

Perisurgery:

- Due to increased risk of deep venous thrombosis (DVT), DVT prophylaxis is recommended [see Dosage and Administration (2.5), Warnings and Precautions (5.1)].

1 INDICATIONS AND USAGE

1.1 Anemia Due to Chronic Kidney Disease

RETACRIT is indicated for the treatment of anemia due to chronic kidney disease (CKD), including patients on dialysis and not on dialysis to decrease the need for red blood cell (RBC) transfusion.

1.2 Anemia Due to Zidovudine in Patients with HIV Infection

RETACRIT is indicated for the treatment of anemia due to zidovudine administered at ≤ 4,200 mg/week in patients with HIV infection with endogenous serum erythropoietin levels of ≤ 500 mUnits/mL.

1.3 Anemia Due to Chemotherapy in Patients with Cancer

RETACRIT is indicated for the treatment of anemia in patients with non-myeloid malignancies where anemia is due to the effect of concomitant myelosuppressive chemotherapy, and upon initiation, there is a minimum of two additional months of planned chemotherapy.

1.4 Reduction of Allogeneic Red Blood Cell Transfusions in Patients Undergoing Elective, Noncardiac, Nonvascular Surgery

RETACRIT is indicated to reduce the need for allogeneic RBC transfusions among patients with perioperative hemoglobin > 10 to ≤ 13 g/dL who are at high risk for perioperative blood loss from elective, noncardiac, nonvascular surgery. RETACRIT is not indicated for patients who are willing to donate autologous blood pre-operatively.

1.5 Limitations of Use

RETACRIT has not been shown to improve quality of life, fatigue, or patient well-being.

RETACRIT is not indicated for use:

- In patients with cancer receiving hormonal agents, biologic products, or radiotherapy, unless also receiving concomitant myelosuppressive chemotherapy.
- In patients with cancer receiving myelosuppressive chemotherapy when the anticipated outcome is cure.
- In patients with cancer receiving myelosuppressive chemotherapy in whom the anemia can be managed by transfusion.
- In patients scheduled for surgery who are willing to donate autologous blood.
- In patients undergoing cardiac or vascular surgery.
- As a substitute for RBC transfusions in patients who require immediate correction of anemia.

2 DOSAGE AND ADMINISTRATION

2.1 Important Dosing Information

Evaluation of Iron Stores and Nutritional Factors

Evaluate the iron status in all patients before and during treatment. Administer supplemental iron therapy when serum ferritin is less than 100 mcg/L or when serum transferrin saturation is less than 20%. The majority of patients with CKD will require supplemental iron during the course of ESA therapy.

Monitoring of Response to Therapy

Correct or exclude other causes of anemia (e.g., vitamin deficiency, metabolic or chronic inflammatory conditions, bleeding, etc.) before initiating RETACRIT. Following initiation of therapy and after each dose adjustment, monitor hemoglobin weekly until the hemoglobin level is stable and sufficient to minimize the need for RBC transfusion.

Selection of Formulation

In pregnant women, lactating women, neonates, and infants use only single-dose vials (the benzyl alcohol-free formulation) [see Contraindications (4) and Use in Specific Populations (8.1, 8.2, and 8.4)].

2.2 Patients with Chronic Kidney Disease

In controlled trials, patients experienced greater risks for death, serious adverse cardiovascular reactions, and stroke when administered ESAs to target a hemoglobin level of greater than 11 g/dL. No trial has identified a hemoglobin target level, ESA dose, or dosing strategy that does not increase these risks. Individualize dosing and use the lowest dose of RETACRIT sufficient to reduce the need for RBC transfusions [see Warnings and Precautions (5.1)]. Physicians and patients should weigh the possible benefits of decreasing transfusions against the increased risks of death and other serious cardiovascular adverse reactions [see Boxed Warning and Clinical Studies (14)].

For all patients with CKD:

When initiating or adjusting therapy, monitor hemoglobin levels at least weekly until stable, then monitor at least monthly. When adjusting therapy consider hemoglobin rate of rise, rate of decline, ESA responsiveness and hemoglobin variability. A single hemoglobin excursion may not require a dosing change.

- Do not increase the dose more frequently than once every 4 weeks. Decreases in dose can occur more frequently. Avoid frequent dose adjustments.
- If the hemoglobin rises rapidly (e.g., more than 1 g/dL in any 2-week period), reduce the dose of RETACRIT by 25% or more as needed to reduce rapid responses.
- For patients who do not respond adequately, if the hemoglobin has not increased by more than 1 g/dL after 4 weeks of therapy, increase the dose by 25%.
- For patients who do not respond adequately over a 12-week escalation period, increasing the RETACRIT dose further is unlikely to improve response and may increase risks. Use the lowest dose that will maintain a hemoglobin level sufficient to reduce the need for RBC transfusions. Evaluate other causes of anemia. Discontinue RETACRIT if responsiveness does not improve.

For adult patients with CKD on dialysis:

- Initiate RETACRIT treatment when the hemoglobin level is less than 10 g/dL.
- If the hemoglobin level approaches or exceeds 11 g/dL, reduce or interrupt the dose of RETACRIT.
- The recommended starting dose for adult patients is 50 to 100 Units/kg 3 times weekly intravenously or subcutaneously. The intravenous route is recommended for patients on hemodialysis.

For adult patients with CKD not on dialysis:

- Consider initiating RETACRIT treatment only when the hemoglobin level is less than 10 g/dL and the following considerations apply:
  - The rate of hemoglobin decline indicates the likelihood of requiring a RBC transfusion
    and,
  - Reducing the risk of alloimmunization and/or other RBC transfusion-related risks is a goal
- If the hemoglobin level exceeds 10 g/dL, reduce or interrupt the dose of RETACRIT, and use the lowest dose of RETACRIT sufficient to reduce the need for RBC transfusions.
- The recommended starting dose for adult patients is 50 to 100 Units/kg 3 times weekly intravenously or subcutaneously.

For pediatric patients with CKD:

- Initiate RETACRIT treatment only when the hemoglobin level is less than 10 g/dL.
- If the hemoglobin level approaches or exceeds 12 g/dL, reduce or interrupt the dose of RETACRIT.
- The recommended starting dose for pediatric patients (ages 1 month or older) is 50 Units/kg 3 times weekly intravenously or subcutaneously.

When treating patients who have chronic kidney disease and cancer, physicians should refer to Warnings and Precautions (5.1 and 5.2).

2.3 Zidovudine-treated Patients with HIV Infection

Starting Dose

The recommended starting dose in adults is 100 Units/kg as an intravenous or subcutaneous injection 3 times per week.

Dose Adjustment

- If hemoglobin does not increase after 8 weeks of therapy, increase RETACRIT dose by approximately 50 to 100 Units/kg at 4- to 8-week intervals until hemoglobin reaches a level needed to avoid RBC transfusions or 300 Units/kg.
- Withhold RETACRIT if hemoglobin exceeds 12 g/dL. Resume therapy at a dose 25% below the previous dose when hemoglobin declines to less than 11 g/dL.

Discontinue RETACRIT if an increase in hemoglobin is not achieved at a dose of 300 Units/kg for 8 weeks.

2.4 Patients on Cancer Chemotherapy

Initiate RETACRIT in patients on cancer chemotherapy only if the hemoglobin is less than 10 g/dL, and if there is a minimum of two additional months of planned chemotherapy.

Use the lowest dose of RETACRIT necessary to avoid RBC transfusions.

Recommended Starting Dose

Adults:

- 150 Units/kg subcutaneously 3 times per week until completion of a chemotherapy course or
- 40,000 Units subcutaneously weekly until completion of a chemotherapy course.

Pediatric Patients (5 to 18 years):

- 600 Units/kg intravenously weekly until completion of a chemotherapy course.

Dose Reduction

Reduce dose by 25% if:

- Hemoglobin increases greater than 1 g/dL in any 2-week period or
- Hemoglobin reaches a level needed to avoid RBC transfusion.

Withhold dose if hemoglobin exceeds a level needed to avoid RBC transfusion. Reinitiate at a dose 25% below the previous dose when hemoglobin approaches a level where RBC transfusions may be required.

Dose Increase

After the initial 4 weeks of RETACRIT therapy, if hemoglobin increases by less than 1 g/dL and remains below 10 g/dL, increase dose to:

- 300 Units/kg three times per week in adults or
- 60,000 Units weekly in adults
- 900 Units/kg (maximum 60,000 Units) weekly in pediatric patients

After 8 weeks of therapy, if there is no response as measured by hemoglobin levels or if RBC transfusions are still required, discontinue RETACRIT.

2.5 Surgery Patients

The recommended RETACRIT regimens are:

- 300 Units/kg per day subcutaneously for 15 days total: administered daily for 10 days before surgery, on the day of surgery, and for 4 days after surgery.
- 600 Units/kg subcutaneously in 4 doses administered 21, 14, and 7 days before surgery and on the day of surgery.

Deep venous thrombosis prophylaxis is recommended during RETACRIT therapy [see Warnings and Precautions (5.1)].

2.6 Preparation and Administration

- Do not shake. Do not use RETACRIT that has been shaken or frozen.
- Protect vials from light.
- Parenteral drug products should be inspected visually for particulate matter and discoloration prior to administration. Do not use any vials exhibiting particulate matter or discoloration.
- Discard unused portions of RETACRIT in preservative-free vials. Do not re-enter preservative-free vials.
- Store unused portions of RETACRIT in multiple-dose vials at 2°C to 8°C (36°F to 46°F). Discard 21 days after initial entry.
- Do not dilute. Do not mix with other drug solutions.
- The vial stopper used for RETACRIT is not made with natural rubber latex.

3 DOSAGE FORMS AND STRENGTHS

Injection:

- 2,000 Units/mL, 3,000 Units/mL, 4,000 Units/mL, and 10,000 Units/mL of RETACRIT as a clear and colorless liquid in single-dose vials.
- 20,000 Units/2 mL (10,000 Units/mL) and 20,000 Units/mL of RETACRIT as a clear and colorless liquid in multiple-dose vials (contains benzyl alcohol).

4 CONTRAINDICATIONS

RETACRIT is contraindicated in patients with:

- Uncontrolled hypertension [see Warnings and Precautions (5.3)].
- Pure red cell aplasia (PRCA) that begins after treatment with RETACRIT or other erythropoietin protein drugs [see Warnings and Precautions (5.6)].
- Serious allergic reactions to RETACRIT or other epoetin alfa products [see Warnings and Precautions (5.7)].

RETACRIT from multiple-dose vials contains benzyl alcohol and is contraindicated in:

- Neonates, infants, pregnant women, and lactating women [see Warnings and Precautions (5.9), Use in Specific Populations (8.1, 8.2 and 8.4)].

5 WARNINGS AND PRECAUTIONS

5.1 Increased Mortality, Myocardial Infarction, Stroke, and Thromboembolism

- In controlled clinical trials of patients with CKD comparing higher hemoglobin targets (13 – 14 g/dL) to lower targets (9 – 11.3 g/dL), epoetin alfa and other ESAs increased the risk of death, myocardial infarction, stroke, congestive heart failure, thrombosis of hemodialysis vascular access, and other thromboembolic events in the higher target groups.
- Using ESAs to target a hemoglobin level of greater than 11 g/dL increases the risk of serious adverse cardiovascular reactions and has not been shown to provide additional benefit [see Clinical Studies (14.1)]. Use caution in patients with coexistent cardiovascular disease and stroke [see Dosage and Administration (2.2)]. Patients with CKD and an insufficient hemoglobin response to ESA therapy may be at even greater risk for cardiovascular reactions and mortality than other patients. A rate of hemoglobin rise of greater than 1 g/dL over 2 weeks may contribute to these risks.
- In controlled clinical trials of patients with cancer, epoetin alfa and other ESAs increased the risks for death and serious adverse cardiovascular reactions. These adverse reactions included myocardial infarction and stroke.
- In controlled clinical trials, ESAs increased the risk of death in patients undergoing coronary artery bypass graft surgery (CABG) and the risk of deep venous thrombosis (DVT) in patients undergoing orthopedic procedures.

The design and overall results of the 3 large trials comparing higher and lower hemoglobin targets are shown in Table 1.

Table 1. Randomized Controlled Trials Showing Adverse Cardiovascular Outcomes in Patients with CKD
 | Normal Hematocrit Study (NHS) (N = 1265) | CHOIR (N = 1432) | TREAT (N = 4038)
Time Period of Trial | 1993 to 1996 | 2003 to 2006 | 2004 to 2009
Population | CKD patients on hemodialysis with coexisting CHF or CAD, hematocrit 30 ± 3% on epoetin alfa | CKD patients not on dialysis with hemoglobin < 11 g/dL not previously administered epoetin alfa | CKD patients not on dialysis with type II diabetes, hemoglobin ≤ 11 g/dL
Hemoglobin Target; Higher vs. Lower (g/dL) | 14.0 vs. 10.0 | 13.5 vs. 11.3 | 13.0 vs. ≥ 9.0
Median (Q1, Q3) Achieved Hemoglobin level (g/dL) | 12.6 (11.6, 13.3) vs. 10.3 (10.0, 10.7) | 13.0 (12.2, 13.4) vs. 11.4 (11.1, 11.6) | 12.5 (12.0, 12.8) vs. 10.6 (9.9, 11.3)
Primary Endpoint | All-cause mortality or non-fatal MI | All-cause mortality, MI, hospitalization for CHF, or stroke | All-cause mortality, MI, myocardial ischemia, heart failure, and stroke
Hazard Ratio or Relative Risk (95% CI) | 1.28 (1.06 – 1.56) | 1.34 (1.03 – 1.74) | 1.05 (0.94 – 1.17)
Adverse Outcome for Higher Target Group | All-cause mortality | All-cause mortality | Stroke
Hazard Ratio or Relative Risk (95% CI) | 1.27 (1.04 – 1.54) | 1.48 (0.97 – 2.27) | 1.92 (1.38 – 2.68)

Patients with Chronic Kidney Disease

Normal Hematocrit Study (NHS): A prospective, randomized, open-label study of 1265 patients with chronic kidney disease on dialysis with documented evidence of congestive heart failure or ischemic heart disease was designed to test the hypothesis that a higher target hematocrit (Hct) would result in improved outcomes compared with a lower target Hct. In this study, patients were randomized to epoetin alfa treatment targeted to a maintenance hemoglobin of either 14 ± 1 g/dL or 10 ± 1 g/dL. The trial was terminated early with adverse safety findings of higher mortality in the high hematocrit target group. Higher mortality (35% vs. 29%) was observed for the patients randomized to a target hemoglobin of 14 g/dL than for the patients randomized to a target hemoglobin of 10 g/dL. For all-cause mortality, the HR=1.27; 95% CI (1.04, 1.54); p=0.018. The incidence of nonfatal myocardial infarction, vascular access thrombosis, and other thrombotic events was also higher in the group randomized to a target hemoglobin of 14 g/dL.

CHOIR: A randomized, prospective trial, 1432 patients with anemia due to CKD who were not undergoing dialysis and who had not previously received epoetin alfa therapy were randomized to epoetin alfa treatment targeting a maintenance hemoglobin concentration of either 13.5 g/dL or 11.3 g/dL. The trial was terminated early with adverse safety findings. A major cardiovascular event (death, myocardial infarction, stroke, or hospitalization for congestive heart failure) occurred in 125 of the 715 patients (18%) in the higher hemoglobin group compared to 97 of the 717 patients (14%) in the lower hemoglobin group [hazard ratio (HR) 1.34, 95% CI: 1.03, 1.74; p=0.03].

TREAT: A randomized, double-blind, placebo-controlled, prospective trial of 4038 patients with: CKD not on dialysis (eGFR of 20 – 60 mL/min), anemia (hemoglobin levels ≤ 11 g/dL), and type 2 diabetes mellitus, patients were randomized to receive either darbepoetin alfa treatment or a matching placebo. Placebo group patients also received darbepoetin alfa when their hemoglobin levels were below 9 g/dL. The trial objectives were to demonstrate the benefit of darbepoetin alfa treatment of the anemia to a target hemoglobin level of 13 g/dL, when compared to a "placebo" group, by reducing the occurrence of either of two primary endpoints: (1) a composite cardiovascular endpoint of all-cause mortality or a specified cardiovascular event (myocardial ischemia, CHF, MI, and CVA) or (2) a composite renal endpoint of all-cause mortality or progression to end stage renal disease. The overall risks for each of the two primary endpoints (the cardiovascular composite and the renal composite) were not reduced with darbepoetin alfa treatment (see Table 1), but the risk of stroke was increased nearly two-fold in the darbepoetin alfa-treated group versus the placebo group: annualized stroke rate 2.1% vs. 1.1%, respectively, HR 1.92; 95% CI: 1.38, 2.68; p < 0.001. The relative risk of stroke was particularly high in patients with a prior stroke: annualized stroke rate 5.2% in the darbepoetin alfa-treated group and 1.9% in the placebo group, HR 3.07; 95% CI: 1.44, 6.54. Also, among darbepoetin alfa-treated subjects with a past history of cancer, there were more deaths due to all causes and more deaths adjudicated as due to cancer, in comparison with the control group.

Patients with Cancer

An increased incidence of thromboembolic reactions, some serious and life-threatening, occurred in patients with cancer treated with ESAs.

In a randomized, placebo-controlled study (Study 2 in Table 2 [see Warnings and Precautions (5.2)]) of 939 women with metastatic breast cancer receiving chemotherapy, patients received either weekly epoetin alfa or placebo for up to a year. This study was designed to show that survival was superior when epoetin alfa was administered to prevent anemia (maintain hemoglobin levels between 12 and 14 g/dL or hematocrit between 36% and 42%). This study was terminated prematurely when interim results demonstrated a higher mortality at 4 months (8.7% vs. 3.4%) and a higher rate of fatal thrombotic reactions (1.1% vs. 0.2%) in the first 4 months of the study among patients treated with epoetin alfa. Based on Kaplan-Meier estimates, at the time of study termination, the 12-month survival was lower in the epoetin alfa group than in the placebo group (70% vs. 76%; HR 1.37, 95% CI: 1.07, 1.75; p = 0.012).

Patients Having Surgery

An increased incidence of deep venous thrombosis (DVT) in patients receiving epoetin alfa undergoing surgical orthopedic procedures was demonstrated [see Adverse Reactions (6.1)]. In a randomized, controlled study, 680 adult patients, not receiving prophylactic anticoagulation and undergoing spinal surgery, were randomized to 4 doses of 600 Units/kg epoetin alfa (7, 14, and 21 days before surgery, and the day of surgery) and standard of care (SOC) treatment (n = 340) or to SOC treatment alone (n = 340). A higher incidence of DVTs, determined by either color flow duplex imaging or by clinical symptoms, was observed in the epoetin alfa group (16 [4.7%] patients) compared with the SOC group (7 [2.1%] patients). In addition to the 23 patients with DVTs included in the primary analysis, 19 [2.8%] patients (n = 680) experienced 1 other thrombovascular event (TVE) each (12 [3.5%] in the epoetin alfa group and 7 [2.1%] in the SOC group). Deep venous thrombosis prophylaxis is strongly recommended when ESAs are used for the reduction of allogeneic RBC transfusions in surgical patients [see Dosage and Administration (2.5)].

Increased mortality was observed in a randomized, placebo-controlled study of epoetin alfa in adult patients who were undergoing CABG surgery (7 deaths in 126 patients randomized to epoetin alfa versus no deaths among 56 patients receiving placebo). Four of these deaths occurred during the period of study drug administration and all 4 deaths were associated with thrombotic events.

5.2 Increased Mortality and/or Increased Risk of Tumor Progression or Recurrence in Patients with Cancer

ESAs resulted in decreased locoregional control/progression-free survival (PFS) and/or overall survival (OS) (see Table 2).

Adverse effects on PFS and/or OS were observed in studies of patients receiving chemotherapy for breast cancer (Studies 1, 2, and 4), lymphoid malignancy (Study 3), and cervical cancer (Study 5); in patients with advanced head and neck cancer receiving radiation therapy (Studies 6 and 7); and in patients with non-small cell lung cancer or various malignancies who were not receiving chemotherapy or radiotherapy (Studies 8 and 9).

Table 2. Randomized, Controlled Studies with Decreased Survival and/or Decreased Locoregional Control
Study/Tumor/(n) | Hemoglobin Target | Achieved Hemoglobin (Median; Q1, Q3 [Q1 = 25th percentile; Q3 = 75th percentile]) | Primary Efficacy Outcome | Adverse Outcome for ESA-containing Arm
Chemotherapy
Study 1 Metastatic breast cancer (n = 2098) | ≤12 g/dL [This study did not include a defined hemoglobin target. Doses were titrated to achieve and maintain the lowest hemoglobin level sufficient to avoid transfusion and not to exceed 12 g/dL.] | 11.6 g/dL; 10.7, 12.1 g/dL | Progression-free survival (PFS) | Decreased progression-free and overall survival
Study 2 Metastatic breast cancer (n = 939) | 12–14 g/dL | 12.9 g/dL; 12.2, 13.3 g/dL | 12-month overall survival | Decreased 12-month survival
Study 3 Lymphoid malignancy (n = 344) | 13–15 g/dL (M) 13–14 g/dL (F) | 11 g/dL; 9.8, 12.1 g/dL | Proportion of patients achieving a hemoglobin response | Decreased overall survival
Study 4 Early breast cancer (n = 733) | 12.5–13 g/dL | 13.1 g/dL; 12.5, 13.7 g/dL | Relapse-free and overall survival | Decreased 3-year relapse-free and overall survival
Study 5 Cervical cancer (n = 114) | 12–14 g/dL | 12.7 g/dL; 12.1, 13.3 g/dL | Progression-free and overall survival and locoregional control | Decreased 3-year progression-free and overall survival and locoregional control
Radiotherapy Alone
Study 6 Head and neck cancer (n = 351) | ≥ 15 g/dL (M) ≥ 14 g/dL (F) | Not available | Locoregional progression-free survival | Decreased 5-year locoregional progression-free and overall survival
Study 7 Head and neck cancer (n = 522) | 14–15.5 g/dL | Not available | Locoregional disease control | Decreased locoregional disease control
No Chemotherapy or Radiotherapy
Study 8 Non-small cell lung cancer (n = 70) | 12–14 g/dL | Not available | Quality of life | Decreased overall survival
Study 9 Non-myeloid malignancy (n = 989) | 12–13 g/dL | 10.6 g/dL; 9.4, 11.8 g/dL | RBC transfusions | Decreased overall survival

Decreased Overall Survival

Study 2 was described in the previous section [see Warnings and Precautions (5.1)]. Mortality at 4 months (8.7% vs. 3.4%) was significantly higher in the epoetin alfa arm. The most common investigator-attributed cause of death within the first 4 months was disease progression; 28 of 41 deaths in the epoetin alfa arm and 13 of 16 deaths in the placebo arm were attributed to disease progression. Investigator-assessed time to tumor progression was not different between the 2 groups. Survival at 12 months was significantly lower in the epoetin alfa arm (70% vs. 76%; HR 1.37, 95% CI: 1.07, 1.75; p = 0.012).

Study 3 was a randomized, double-blind study (darbepoetin alfa vs. placebo) conducted in 344 anemic patients with lymphoid malignancy receiving chemotherapy. With a median follow-up of 29 months, overall mortality rates were significantly higher among patients randomized to darbepoetin alfa as compared to placebo (HR 1.36, 95% CI: 1.02, 1.82).

Study 8 was a multicenter, randomized, double-blind study (epoetin alfa vs. placebo) in which patients with advanced non-small cell lung cancer receiving only palliative radiotherapy or no active therapy were treated with epoetin alfa to achieve and maintain hemoglobin levels between 12 and 14 g/dL. Following an interim analysis of 70 patients (planned accrual 300 patients), a significant difference in survival in favor of the patients in the placebo arm of the study was observed (median survival 63 vs. 129 days; HR 1.84; p = 0.04).

Study 9 was a randomized, double-blind study (darbepoetin alfa vs. placebo) in 989 anemic patients with active malignant disease, neither receiving nor planning to receive chemotherapy or radiation therapy. There was no evidence of a statistically significant reduction in proportion of patients receiving RBC transfusions. The median survival was shorter in the darbepoetin alfa treatment group than in the placebo group (8 months vs. 10.8 months; HR 1.30, 95% CI: 1.07, 1.57).

Decreased Progression-free Survival and Overall Survival

Study 1 was a randomized, open-label, multicenter study in 2,098 anemic women with metastatic breast cancer, who received first line or second line chemotherapy. This was a non-inferiority study designed to rule out a 15% risk increase in tumor progression or death of epoetin alfa plus standard of care (SOC) as compared with SOC alone. At the time of clinical data cutoff, the median progression free survival (PFS) per investigator assessment of disease progression was 7.4 months in each arm (HR 1.09, 95% CI: 0.99, 1.20), indicating the study objective was not met. There were more deaths from disease progression in the epoetin alfa plus SOC arm (59% vs. 56%) and more thrombotic vascular events in the epoetin alfa plus SOC arm (3% vs. 1%). At the final analysis, 1653 deaths were reported (79.8% subjects in the epoetin alfa plus SOC group and 77.8% subjects in the SOC group). Median overall survival in the epoetin alfa plus SOC group was 17.8 months compared with 18.0 months in the SOC alone group (HR 1.07, 95% CI: 0.97, 1.18).

Study 4 was a randomized, open-label, controlled, factorial design study in which darbepoetin alfa was administered to prevent anemia in 733 women receiving neo-adjuvant breast cancer treatment. A final analysis was performed after a median follow-up of approximately 3 years. The 3-year survival rate was lower (86% vs. 90%; HR 1.42, 95% CI: 0.93, 2.18) and the 3-year relapse-free survival rate was lower (72% vs. 78%; HR 1.33, 95% CI: 0.99, 1.79) in the darbepoetin alfa-treated arm compared to the control arm.

Study 5 was a randomized, open-label, controlled study that enrolled 114 of a planned 460 cervical cancer patients receiving chemotherapy and radiotherapy. Patients were randomized to receive epoetin alfa to maintain hemoglobin between 12 and 14 g/dL or to RBC transfusion support as needed. The study was terminated prematurely due to an increase in thromboembolic adverse reactions in epoetin alfa-treated patients compared to control (19% vs. 9%). Both local recurrence (21% vs. 20%) and distant recurrence (12% vs. 7%) were more frequent in epoetin alfa-treated patients compared to control. Progression-free survival at 3 years was lower in the epoetin alfa-treated group compared to control (59% vs. 62%; HR 1.06, 95% CI: 0.58, 1.91). Overall survival at 3 years was lower in the epoetin alfa-treated group compared to control (61% vs. 71%; HR 1.28, 95% CI: 0.68, 2.42).

Study 6 was a randomized, placebo-controlled study in 351 head and neck cancer patients where epoetin beta or placebo was administered to achieve target hemoglobins ≥ 14 and ≥ 15 g/dL for women and men, respectively. Locoregional progression-free survival was significantly shorter in patients receiving epoetin beta (HR 1.62, 95% CI: 1.22, 2.14; p = 0.0008) with medians of 406 days and 745 days in the epoetin beta and placebo arms, respectively. Overall survival was significantly shorter in patients receiving epoetin beta (HR 1.39, 95% CI: 1.05, 1.84; p = 0.02).

Decreased Locoregional Control

Study 7 was a randomized, open-label, controlled study conducted in 522 patients with primary squamous cell carcinoma of the head and neck receiving radiation therapy alone (no chemotherapy) who were randomized to receive darbepoetin alfa to maintain hemoglobin levels of 14 to 15.5 g/dL or no darbepoetin alfa. An interim analysis performed on 484 patients demonstrated that locoregional control at 5 years was significantly shorter in patients receiving darbepoetin alfa (RR 1.44, 95% CI: 1.06, 1.96; p = 0.02). Overall survival was shorter in patients receiving darbepoetin alfa (RR 1.28, 95% CI: 0.98, 1.68; p = 0.08).

5.3 Hypertension

RETACRIT is contraindicated in patients with uncontrolled hypertension. Following initiation and titration of epoetin alfa, approximately 25% of patients on dialysis required initiation of or increases in antihypertensive therapy; hypertensive encephalopathy and seizures have been reported in patients with CKD receiving epoetin alfa.

Appropriately control hypertension prior to initiation of and during treatment with RETACRIT. Reduce or withhold RETACRIT if blood pressure becomes difficult to control. Advise patients of the importance of compliance with antihypertensive therapy and dietary restrictions [see Patient Counseling Information (17)].

5.4 Seizures

Epoetin alfa products, including RETACRIT, increase the risk of seizures in patients with CKD. During the first several months following initiation of RETACRIT, monitor patients closely for premonitory neurologic symptoms. Advise patients to contact their healthcare practitioner for new-onset seizures, premonitory symptoms or change in seizure frequency.

5.5 Lack or Loss of Hemoglobin Response to RETACRIT

For lack or loss of hemoglobin response to RETACRIT, initiate a search for causative factors (e.g., iron deficiency, infection, inflammation, bleeding). If typical causes of lack or loss of hemoglobin response are excluded, evaluate for PRCA [see Warnings and Precautions (5.6)]. In the absence of PRCA, follow dosing recommendations for management of patients with an insufficient hemoglobin response to RETACRIT therapy [see Dosage and Administration (2.2)].

5.6 Pure Red Cell Aplasia

Cases of PRCA and of severe anemia, with or without other cytopenias that arise following the development of neutralizing antibodies to erythropoietin have been reported in patients treated with epoetin alfa. This has been reported predominantly in patients with CKD receiving ESAs by subcutaneous administration. PRCA has also been reported in patients receiving ESAs for anemia related to hepatitis C treatment (an indication for which RETACRIT is not approved).

If severe anemia and low reticulocyte count develop during treatment with RETACRIT, withhold RETACRIT and evaluate patients for neutralizing antibodies to erythropoietin. Contact Hospira, Inc., a Pfizer Company (1-800-438-1985) to perform assays for binding and neutralizing antibodies. Permanently discontinue RETACRIT in patients who develop PRCA following treatment with RETACRIT or other erythropoietin protein drugs. Do not switch patients to other ESAs.

5.7 Serious Allergic Reactions

Serious allergic reactions, including anaphylactic reactions, angioedema, bronchospasm, skin rash, and urticaria may occur with epoetin alfa products. Immediately and permanently discontinue RETACRIT and administer appropriate therapy if a serious allergic or anaphylactic reaction occurs.

5.8 Severe Cutaneous Reactions

Blistering and skin exfoliation reactions including Erythema multiforme and Stevens-Johnson Syndrome (SJS)/Toxic Epidermal Necrolysis (TEN), have been reported in patients treated with ESAs (including epoetin alfa) in the postmarketing setting. Discontinue RETACRIT therapy immediately if a severe cutaneous reaction, such as SJS/TEN, is suspected.

5.9 Risk of Serious Adverse Reactions Due to Benzyl Alcohol Preservative

RETACRIT from multiple-dose vials contains benzyl alcohol and is contraindicated for use in neonates, infants, pregnant women, and lactating women [see Contraindications (4)]. In addition, do not mix RETACRIT with bacteriostatic saline (which also contains benzyl alcohol) when administering RETACRIT to these patient populations [see Dosage and Administration (2)].

Serious and fatal reactions including "gasping syndrome" can occur in neonates and infants treated with benzyl alcohol-preserved drugs, including RETACRIT multiple-dose vials. The "gasping syndrome" is characterized by central nervous system depression, metabolic acidosis, and gasping respirations. There is a potential for similar risks to fetuses and infants exposed to benzyl alcohol in utero or in breast-fed milk, respectively. RETACRIT multiple-dose vials contain 8.5 mg of benzyl alcohol per mL. The minimum amount of benzyl alcohol at which serious adverse reactions may occur is not known [see Use in Specific Populations (8.1, 8.2, and 8.4)].

5.10 Risk in Patients with Phenylketonuria

Phenylalanine can be harmful to patients with phenylketonuria (PKU). RETACRIT contains phenylalanine, a component of aspartame. Each 1 mL single-dose vial of 2,000, 3,000, 4,000, and 10,000 Units of epoetin alfa-epbx injection contains 0.5 mg of phenylalanine. Before prescribing RETACRIT to a patient with PKU, consider the combined daily amount of phenylalanine from all sources, including RETACRIT.

5.11 Dialysis Management

Patients may require adjustments in their dialysis prescriptions after initiation of RETACRIT. Patients receiving RETACRIT may require increased anticoagulation with heparin to prevent clotting of the extracorporeal circuit during hemodialysis.

6 ADVERSE REACTIONS

The following serious adverse reactions are discussed in greater detail in other sections of the label:

- Increased Mortality, Myocardial Infarction, Stroke, and Thromboembolism [see Warnings and Precautions (5.1)]
- Increased mortality and/or increased risk of tumor progression or recurrence in Patients with Cancer [see Warnings and Precautions (5.2)]
- Hypertension [see Warnings and Precautions (5.3)]
- Seizures [see Warnings and Precautions (5.4)]
- PRCA [see Warnings and Precautions (5.6)]
- Serious allergic reactions [see Warnings and Precautions (5.7)]
- Severe Cutaneous Reactions [see Warnings and Precautions (5.8)]

6.1 Clinical Trials Experience

Because clinical trials are conducted under widely varying conditions, adverse reaction rates observed in the clinical trials of a drug cannot be directly compared to rates in the clinical trials of other drugs and may not reflect the rates observed in practice.

Patients with Chronic Kidney Disease

Adult Patients

Three double-blind, placebo-controlled studies, including 244 patients with CKD on dialysis, were used to identify the adverse reactions to epoetin alfa. In these studies, the mean age of patients was 48 years (range: 20 to 80 years). One hundred and thirty-three (55%) patients were men. The racial distribution was as follows: 177 (73%) patients were white, 48 (20%) patients were black, 4 (2%) patients were Asian, 12 (5%) patients were other, and racial information was missing for 3 (1%) patients.

Two double-blind, placebo-controlled studies, including 210 patients with CKD not on dialysis, were used to identify the adverse reactions to epoetin alfa. In these studies, the mean age of patients was 57 years (range: 24 to 79 years). One hundred and twenty-one (58%) patients were men. The racial distribution was as follows: 164 (78%) patients were white, 38 (18%) patients were black, 3 (1%) patients were Asian, 3 (1%) patients were other, and racial information was missing for 2 (1%) patients.

The adverse reactions with a reported incidence of ≥ 5% in epoetin alfa-treated patients and that occurred at a ≥ 1% higher frequency than in placebo-treated patients are shown in the table below:

Table 3. Adverse Reactions in Patients with CKD on Dialysis
Adverse Reaction | Epoetin alfa-treated Patients (n = 148) | Placebo-treated Patients (n = 96)
Hypertension | 27.7% | 12.5%
Arthralgia | 16.2% | 3.1%
Muscle spasm | 7.4% | 6.3%
Pyrexia | 10.1% | 8.3%
Dizziness | 9.5% | 8.3%
Medical Device Malfunction (artificial kidney clotting during dialysis) | 8.1% | 4.2%
Vascular Occlusion (vascular access thrombosis) | 8.1% | 2.1%
Upper respiratory tract infection | 6.8% | 5.2%

An additional serious adverse reaction that occurred in less than 5% of epoetin alfa-treated dialysis patients and greater than placebo was thrombosis (2.7% epoetin alfa and 1% placebo) [see Warnings and Precautions (5.1)].

The adverse reactions with a reported incidence of ≥ 5% in epoetin alfa-treated patients and that occurred at a ≥ 1% higher frequency than in placebo-treated patients are shown in the table below:

Table 4. Adverse Reactions in Patients with CKD Not on Dialysis
Adverse Reactions | Epoetin alfa-treated Patients (n = 131) | Placebo-treated Patients (n = 79)
Hypertension | 13.7% | 10.1%
Arthralgia | 12.2% | 7.6%

Additional serious adverse reactions that occurred in less than 5% of epoetin alfa-treated patients not on dialysis and greater than placebo were erythema (0.8% epoetin alfa and 0% placebo) and myocardial infarction (0.8% epoetin alfa and 0% placebo) [see Warnings and Precautions (5.1)].

Pediatric Patients

In pediatric patients with CKD on dialysis, the pattern of adverse reactions was similar to that found in adults.

Zidovudine-treated Patients with HIV Infection

A total of 297 zidovudine-treated patients with HIV infection were studied in 4 placebo-controlled studies. A total of 144 (48%) patients were randomly assigned to receive epoetin alfa and 153 (52%) patients were randomly assigned to receive placebo. Epoetin alfa was administered at doses between 100 and 200 Units/kg 3 times weekly subcutaneously for up to 12 weeks.

For the combined epoetin alfa treatment groups, a total of 141 (98%) men and 3 (2%) women between the ages of 24 and 64 years were enrolled. The racial distribution of the combined epoetin alfa treatment groups was as follows: 129 (90%) white, 8 (6%) black, 1 (1%) Asian, and 6 (4%) other.

In double-blind, placebo-controlled studies of 3 months duration involving approximately 300 zidovudine-treated patients with HIV infection, adverse reactions with an incidence of ≥ 1% in patients treated with epoetin alfa were:

Table 5. Adverse Reactions in Zidovudine-treated Patients with HIV Infection
Adverse Reaction | Epoetin alfa (n = 144) | Placebo (n = 153)
Pyrexia | 42% | 34%
Cough | 26% | 14%
Rash | 19% | 7%
Injection site irritation | 7% | 4%
Urticaria | 3% | 1%
Respiratory tract congestion | 1% | Not reported
Pulmonary embolism | 1% | Not reported

Patients with Cancer on Chemotherapy

The data below were obtained in Study C1, a 16-week, double-blind, placebo-controlled study that enrolled 344 patients with anemia secondary to chemotherapy. There were 333 patients who were evaluable for safety; 168 of 174 patients (97%) randomized to epoetin alfa received at least 1 dose of study drug, and 165 of 170 patients (97%) randomized to placebo received at least 1 placebo dose. For the once weekly epoetin alfa treatment group, a total of 76 men (45%) and 92 women (55%) between the ages of 20 and 88 years were treated. The racial distribution of the epoetin alfa-treatment group was 158 white (94%) and 10 black (6%). Epoetin alfa was administered once weekly for an average of 13 weeks at a dose of 20,000 to 60,000 IU subcutaneously (mean weekly dose was 49,000 IU).

The adverse reactions with a reported incidence of ≥ 5% in epoetin alfa-treated patients that occurred at a higher frequency than in placebo-treated patients are shown in the table below:

Table 6. Adverse Reactions in Patients with Cancer
Adverse Reaction | Epoetin alfa (n = 168) | Placebo (n = 165)
Nausea | 35% | 30%
Vomiting | 20% | 16%
Myalgia | 10% | 5%
Arthralgia | 10% | 6%
Stomatitis | 10% | 8%
Cough | 9% | 7%
Weight decrease | 9% | 5%
Leukopenia | 8% | 7%
Bone pain | 7% | 4%
Rash | 7% | 5%
Hyperglycemia | 6% | 4%
Insomnia | 6% | 2%
Headache | 5% | 4%
Depression | 5% | 4%
Dysphagia | 5% | 2%
Hypokalemia | 5% | 3%
Thrombosis | 5% | 3%

Surgery Patients

Four hundred sixty-one patients undergoing major orthopedic surgery were studied in a placebo-controlled study (S1) and a comparative dosing study (2 dosing regimens, S2). A total of 358 patients were randomly assigned to receive epoetin alfa and 103 (22%) patients were randomly assigned to receive placebo. Epoetin alfa was administered daily at a dose of 100 to 300 IU/kg subcutaneously for 15 days or at 600 IU/kg once weekly for 4 weeks.

For the combined epoetin alfa treatment groups, a total of 90 (25%) men and 268 (75%) women between the ages of 29 and 89 years were enrolled. The racial distribution of the combined epoetin alfa treatment groups was as follows: 288 (80%) white, 64 (18%) black, 1 (< 1%) Asian, and 5 (1%) other.

The adverse reactions with a reported incidence of ≥ 1% in epoetin alfa-treated patients that occurred at a higher frequency than in placebo-treated patients are shown in the table below:

Table 7. Adverse Reactions in Surgery Patients
Adverse Reaction | Study S1 |  |  | Study S2
Adverse Reaction | Epoetin alfa 300 U/kg | Epoetin alfa 100 U/kg | Placebo | Epoetin alfa 600 U/kg × 4 weeks | Epoetin alfa 300 U/kg × 15 days
Adverse Reaction | (n = 112) [Study included patients undergoing orthopedic surgery treated with epoetin alfa or placebo for 15 days.] | (n = 101) | (n = 103) | (n = 73) [Study included patients undergoing orthopedic surgery treated with epoetin alfa 600 U/kg weekly for 4 weeks or 300 U/kg daily for 15 days.] | (n = 72)
Nausea | 47% | 43% | 45% | 45% | 56%
Vomiting | 21% | 12% | 14% | 19% | 28%
Pruritus | 16% | 16% | 14% | 12% | 21%
Headache | 13% | 11% | 9% | 10% | 18%
Injection site pain | 13% | 9% | 8% | 12% | 11%
Chills | 7% | 4% | 1% | 1% | 0%
Deep vein thrombosis | 6% | 3% | 3% | 0% [DVTs were determined by clinical symptoms.] | 0%
Cough | 5% | 4% | 0% | 4% | 4%
Hypertension | 5% | 3% | 5% | 5% | 6%
Rash | 2% | 2% | 1% | 3% | 3%
Edema | 1% | 2% | 2% | 1% | 3%

6.2 Postmarketing Experience

The following adverse reactions have been identified during post-approval use of epoetin alfa.

Because these reactions are reported voluntarily from a population of uncertain size, it is not always possible to reliably estimate their frequency or establish a causal relationship to drug exposure.

- Seizures [see Warnings and Precautions (5.4)]
- PRCA [see Warnings and Precautions (5.6)]
- Serious allergic reactions [see Warnings and Precautions (5.7)]
- Injection site reactions, including irritation and pain
- Porphyria
- Severe Cutaneous Reactions [see Warnings and Precautions (5.8)]

6.3 Immunogenicity

The observed incidence of anti-drug antibodies is highly dependent on the sensitivity and specificity of the assay. Differences in assay methods preclude meaningful comparisons of the incidence of anti-drug antibodies in the studies described below with the incidence of anti-drug antibodies in other studies, including those of epoetin alfa or of other epoetin alfa products.

Neutralizing antibodies to epoetin alfa that cross-react with endogenous erythropoietin and other ESAs can result in PRCA or severe anemia (with or without other cytopenias) [see Warnings and Precautions (5.6)].

8 USE IN SPECIFIC POPULATIONS

8.1 Pregnancy

Risk Summary

RETACRIT from multiple-dose vials contains benzyl alcohol and is contraindicated in pregnant women [see Contraindications (4)]. When therapy with RETACRIT is needed during pregnancy, use a benzyl alcohol-free formulation (i.e., single-dose vial). Do not mix RETACRIT with bacteriostatic saline when administering to pregnant women because it contains benzyl alcohol (see Clinical Considerations) [see Dosage and Administration (2.1)].

The limited available data on epoetin alfa use in pregnant women are insufficient to determine a drug-associated risk of adverse developmental outcomes. In animal reproductive and developmental toxicity studies, adverse fetal effects including embryo-fetal death, skeletal anomalies, and growth defects occurred when pregnant rats received epoetin alfa at doses approximating the clinical recommended starting doses (see Data). Consider the benefits and risks of RETACRIT single-dose vials for the mother and possible risks to the fetus when prescribing RETACRIT to a pregnant woman.

The estimated background risk of major birth defects and miscarriage for the indicated population is unknown. All pregnancies have a background risk of birth defect, loss, or other adverse outcomes. In the U.S. general population, the estimated background risks of major birth defects and miscarriage in clinically recognized pregnancies is 2–4% and 15–20%, respectively.

Clinical Considerations

Fetal/Neonatal Adverse Reactions

The multiple-dose vials of RETACRIT contain benzyl alcohol. The preservative benzyl alcohol has been associated with serious adverse reactions and death when administered intravenously to neonates and infants [see Warnings and Precautions (5.9), Use in Specific Populations (8.4)]. There is a potential for similar risks to fetuses exposed to benzyl alcohol in utero.

Data

Human Data

There are reports of pregnant women with anemia alone or anemia associated with severe renal disease and other hematologic disorders who received epoetin alfa. Polyhydramnios and intrauterine growth restriction were reported in women with chronic renal disease, which is associated with an increased risk for these adverse pregnancy outcomes. Due to the limited number of exposed pregnancies and multiple confounding factors (such as underlying maternal conditions, other maternal medications, and gestational timing of exposure), these published case reports and studies do not reliably estimate the frequency, presence or absence of adverse outcomes.

Animal Data

When rats received epoetin alfa at doses greater than or equal to 100 Units/kg/day during mating and through early pregnancy (dosing stopped prior to organogenesis), there were slight increases in the incidences of pre- and post-implantation loss, and a decrease in live fetuses in the presence of maternal toxicity (red limbs/pinna, focal splenic capsular toxicity, increased organ weights). This animal dose level of 100 Units/kg/day may approximate the clinical recommended starting dose, depending on the treatment indication. When pregnant rats and rabbits received intravenous doses of up to 500 mg/kg/day of epoetin alfa only during organogenesis (gestational days 7 to 17 in rats and gestational days 6 to 18 in rabbits), no teratogenic effects were observed in the offspring. The offspring (F1 generation) of the treated rats were observed postnatally; rats from the F1 generation reached maturity and were mated; no epoetin alfa-related effects were apparent for their offspring (F2 generation fetuses).

When pregnant rats received epoetin alfa at doses of 500 Units/kg/day late in pregnancy (after the period of organogenesis from day 17 of gestation through day 21 of lactation), pups exhibited decreased number of caudal vertebrae, decreased body weight gain, and delayed appearance of abdominal hair, eyelid opening, and ossification in the presence of maternal toxicity (red limbs/pinna, increased organ weights). This animal dose level of 500 U/kg/day is approximately five times the clinical recommended starting dose depending on the patient's treatment indication.

8.2 Lactation

Risk Summary

RETACRIT from multiple-dose vials contains benzyl alcohol and is contraindicated in lactating women [see Contraindications (4), Warnings and Precautions (5.9)]. Advise a lactating woman not to breastfeed for at least 2 weeks after the last dose. The preservative benzyl alcohol has been associated with serious adverse reactions and death when administered intravenously to neonates and infants [see Use in Specific Populations (8.4)]. There is a potential for similar risks to infants exposed to benzyl alcohol through human milk.

Do not mix RETACRIT with bacteriostatic saline containing benzyl alcohol, if administering RETACRIT to a lactating woman [see Dosage and Administration (2.1)].

There is no information regarding the presence of epoetin alfa products in human milk, the effects on the breastfed infant, or the effects on milk production. However, endogenous erythropoietin is present in human milk. Because many drugs are present in human milk, caution should be exercised when RETACRIT is administered to a lactating woman.

8.4 Pediatric Use

The multiple-dose vials are formulated with benzyl alcohol and are contraindicated for use in neonates and infants [see Contraindications (4), Warnings and Precautions (5.9)]. When therapy with RETACRIT is needed in neonates and infants, use the single-dose vial, which is a benzyl alcohol-free formulation. Do not mix the single-dose vials with bacteriostatic saline when administering RETACRIT to neonates or infants because it contains benzyl alcohol [see Dosage and Administration (2.6)].

Serious adverse reactions including fatal reactions and the "gasping syndrome" occurred in premature neonates and infants in the neonatal intensive care unit who received drugs containing benzyl alcohol as a preservative. In these cases, benzyl alcohol dosages of 99 to 234 mg/kg/day produced high levels of benzyl alcohol and its metabolites in the blood and urine (blood levels of benzyl alcohol were 0.61 to 1.378 mmol/L). Additional adverse reactions included gradual neurological deterioration, seizures, intracranial hemorrhage, hematologic abnormalities, skin breakdown, hepatic and renal failure, hypotension, bradycardia, and cardiovascular collapse. Preterm, low birth weight infants may be more likely to develop these reactions because they may be less able to metabolize benzyl alcohol. The minimum amount of benzyl alcohol at which serious adverse reactions may occur is not known [see Warnings and Precautions (5.9)].

Pediatric Patients with CKD

RETACRIT is indicated in pediatric patients, ages 1 month to 16 years of age, for the treatment of anemia associated with CKD requiring dialysis. Safety and effectiveness in pediatric patients less than 1 month old have not been established [see Clinical Studies (14.1)].

Use of RETACRIT in pediatric patients with CKD not requiring dialysis is supported by efficacy of epoetin alfa in pediatric patients requiring dialysis. The mechanism of action of epoetin alfa products is the same for these two populations. Published literature also has reported the use of epoetin alfa in pediatric patients with CKD not requiring dialysis. Dose-dependent increases in hemoglobin and hematocrit were observed with reductions in transfusion requirements.

The safety data from the pediatric studies and postmarketing reports are similar to those obtained from the studies of epoetin alfa in adult patients with CKD [see Warnings and Precautions (5) and Adverse Reactions (6.1)]. Postmarketing reports do not indicate a difference in safety profiles in pediatric patients with CKD requiring dialysis and not requiring dialysis.

Pediatric Patients with Cancer on Chemotherapy

RETACRIT is indicated in patients 5 to 18 years old for the treatment of anemia due to concomitant myelosuppressive chemotherapy. Safety and effectiveness in pediatric patients less than 5 years of age have not been established [see Clinical Studies (14.3)]. The safety data from these studies are similar to those obtained from the studies of epoetin alfa in adult patients with cancer [see Warnings and Precautions (5.1, 5.2) and Adverse Reactions (6.1)].

Pediatric Patients with HIV Infection Receiving Zidovudine

Published literature has reported the use of epoetin alfa in 20 zidovudine-treated, anemic, pediatric patients with HIV infection, ages 8 months to 17 years, treated with 50 to 400 Units/kg subcutaneously or intravenously 2 to 3 times per week. Increases in hemoglobin levels and in reticulocyte counts and decreases in or elimination of RBC transfusions were observed.

Pharmacokinetics in Neonates

Limited pharmacokinetic data from a study of 7 preterm, very low birth weight neonates and 10 healthy adults given intravenous erythropoietin suggested that distribution volume was approximately 1.5 to 2 times higher in the preterm neonates than in the healthy adults, and clearance was approximately 3 times higher in the preterm neonates than in the healthy adults.

8.5 Geriatric Use

Of the 4553 patients who received epoetin alfa in the 6 studies for treatment of anemia due to CKD not receiving dialysis, 2726 (60%) were age 65 years and over, while 1418 (31%) were 75 years and over. Of the 757 patients who received epoetin alfa in the 3 studies of CKD patients on dialysis, 361 (47%) were age 65 years and over, while 100 (13%) were 75 years and over. No differences in safety or effectiveness were observed between geriatric and younger patients. Dose selection and adjustment for an elderly patient should be individualized to achieve and maintain the target hemoglobin [see Dosage and Administration (2)].

Among 778 patients enrolled in the 3 clinical studies of epoetin alfa for the treatment of anemia due to concomitant chemotherapy, 419 received epoetin alfa and 359 received placebo. Of the 419 who received epoetin alfa, 247 (59%) were age 65 years and over, while 78 (19%) were 75 years and over. No overall differences in safety or effectiveness were observed between geriatric and younger patients. The dose requirements for epoetin alfa in geriatric and younger patients within the 3 studies were similar.

Among 1731 patients enrolled in the 6 clinical studies of epoetin alfa for reduction of allogeneic RBC transfusions in patients undergoing elective surgery, 1085 received epoetin alfa and 646 received placebo or standard of care treatment. Of the 1085 patients who received epoetin alfa, 582 (54%) were age 65 years and over, while 245 (23%) were 75 years and over. No overall differences in safety or effectiveness were observed between geriatric and younger patients. The dose requirements for epoetin alfa in geriatric and younger patients within the 4 studies using the 3 times weekly schedule and 2 studies using the weekly schedule were similar.

Insufficient numbers of patients age 65 years or older were enrolled in clinical studies of epoetin alfa for the treatment of patients treated with zidovudine for HIV infection to determine whether they respond differently from younger patients.

9 DRUG ABUSE AND DEPENDENCE

9.1 Controlled Substance

RETACRIT contains epoetin alfa-epbx, which is not a controlled substance.

9.2 Abuse

Abuse is the intentional, non-therapeutic use of a drug, even once, for its desirable psychological or physiological effects. Abuse of RETACRIT may be seen in athletes for the effects on erythropoiesis. Abuse of drugs that increase erythropoiesis, such as RETACRIT, by healthy persons may lead to life-threatening cardiovascular complications (e.g., stroke, myocardial infarction, and thromboembolism) [see Warnings and Precautions (5.1)].

In animal studies, epoetin alfa did not distribute to the CNS nor produce behavioral effects that are consistent with CNS activity.

10 OVERDOSAGE

RETACRIT overdosage can cause hemoglobin levels above the desired level, which should be managed with discontinuation or reduction of RETACRIT dosage and/or with phlebotomy, as clinically indicated [see Clinical Pharmacology (12.2)]. Cases of severe hypertension have been observed following overdose with ESAs [see Warnings and Precautions (5.3)].

11 DESCRIPTION

Epoetin alfa-epbx is an erythropoiesis-stimulating agent. Epoetin alfa-epbx is a 165-amino acid glycoprotein manufactured by recombinant DNA technology. It has a molecular weight of approximately 30,400 daltons and is produced in Chinese Hamster Ovary (CHO) cell line. The product contains the identical amino acid sequence of isolated natural erythropoietin.

RETACRIT (epoetin alfa-epbx) injection for intravenous or subcutaneous administration is a sterile, clear, colorless solution in vials in multiple formulations.

Each 1 mL single-dose vial of 2,000, 3,000, 4,000, and 10,000 Units of epoetin alfa-epbx contains calcium chloride dihydrate (0.01 mg), glycine (7.5 mg), isoleucine (1 mg), leucine (1 mg), L-glutamic acid (0.25 mg), phenylalanine (0.5 mg), polysorbate 20 (0.1 mg), sodium chloride (2.4 mg), sodium phosphate dibasic anhydrous (4.9 mg), sodium phosphate monobasic monohydrate (1.3 mg), and threonine (0.25 mg), in Water for Injection, USP. Sodium hydroxide and hydrochloric acid may be added to adjust the pH (pH 7.0 – 7.5).

Each 1 mL multiple-dose vial of 20,000 Units of epoetin alfa-epbx contains benzyl alcohol (8.5 mg), L-methionine (0.45 mg), polysorbate 20 (0.04 mg), sodium phosphate dibasic anhydrous (0.09 mg), sodium phosphate monobasic monohydrate (2.67 mg), and sucrose (60 mg) in Water for Injection, USP. Sodium hydroxide and hydrochloric acid may be added to adjust the pH (pH 5.6 – 6.6).

Each 2 mL multiple-dose vial of 20,000 Units (10,000 Units/mL) of epoetin alfa-epbx contains benzyl alcohol (17 mg), L-methionine (0.9 mg), polysorbate 20 (0.08 mg), sodium phosphate dibasic anhydrous (0.18 mg), sodium phosphate monobasic monohydrate (5.34 mg), and sucrose (120 mg) in Water for Injection, USP. Sodium hydroxide and hydrochloric acid may be added to adjust the pH (pH 5.6 – 6.6).

12 CLINICAL PHARMACOLOGY

12.1 Mechanism of Action

Epoetin alfa products stimulate erythropoiesis by the same mechanism as endogenous erythropoietin.

12.2 Pharmacodynamics

Epoetin alfa products increase the reticulocyte count within 10 days of initiation, followed by increases in the RBC count, hemoglobin, and hematocrit, usually within 2 to 6 weeks. The rate of hemoglobin increase varies among patients and is dependent upon the dose of epoetin alfa products administered. For correction of anemia in hemodialysis patients, a greater biologic response is not observed at doses exceeding 300 Units/kg 3 times weekly.

12.3 Pharmacokinetics

In adult and pediatric patients with CKD, the elimination half-life (t1/2) of plasma erythropoietin after intravenous administration of epoetin alfa ranged from 4 to 13 hours. After subcutaneous administration, Cmax was achieved within 5 to 24 hours. The t1/2 in adult patients with serum creatinine greater than 3 mg/dL was similar between those not on dialysis and those maintained on dialysis. The pharmacokinetic data indicate no apparent difference in epoetin alfa t1/2 among adult patients above or below 65 years of age.

A pharmacokinetic study comparing 150 Units/kg subcutaneous 3 times weekly to 40,000 Units subcutaneous weekly dosing regimen was conducted for 4 weeks in healthy subjects (n = 12) and for 6 weeks in anemic cancer patients (n = 32) receiving cyclic chemotherapy. There was no accumulation of serum erythropoietin after the 2 dosing regimens during the study period. The 40,000 Units weekly regimen had a higher Cmax (3- to 7-fold), longer Tmax (2- to 3-fold), higher AUC0–168 h (2- to 3-fold) of erythropoietin and lower clearance (CL) (50%) than the 150 Units/kg 3 times weekly regimen. In anemic cancer patients, the average t1/2 was similar (40 hours with range of 16 to 67 hours) after both dosing regimens. After the 150 Units/kg 3 times weekly dosing, the values of Tmax and CL were similar (13.3 ± 12.4 vs. 14.2 ± 6.7 hours, and 20.2 ± 15.9 vs. 23.6 ± 9.5 mL/hr/kg) between week 1 when patients were receiving chemotherapy (n = 14) and week 3 when patients were not receiving chemotherapy (n = 4). Differences were observed after the 40,000 Units weekly dosing with longer Tmax (38 ± 18 hours) and lower CL (9.2 ± 4.7 mL/hr/kg) during week 1 when patients were receiving chemotherapy (n = 18) compared with those (22 ± 4.5 hours, 13.9 ± 7.6 mL/hr/kg, respectively) during week 3 when patients were not receiving chemotherapy (n = 7).

The pharmacokinetic profile of epoetin alfa in pediatric patients appeared similar to that of adults.

The pharmacokinetics of epoetin alfa products has not been studied in patients with HIV infection.

13 NONCLINICAL TOXICOLOGY

13.1 Carcinogenesis, Mutagenesis, Impairment of Fertility

The carcinogenic potential of epoetin alfa products has not been evaluated.

Epoetin alfa was not mutagenic or clastogenic under the conditions tested: epoetin alfa was negative in the in vitro bacterial reverse mutation assay (Ames test), in the in vitro mammalian cell gene mutation assay (the hypoxanthine-guanine phosphoribosyl transferase [HGPRT] locus), in an in vitro chromosomal aberration assay in mammalian cells, and in the in vivo mouse micronucleus assay.

When administered intravenously to male and female rats prior to and during mating, and to females through the beginning of implantation (up to gestational day 7; dosing stopped prior to the beginning of organogenesis), doses of 100 and 500 Units/kg/day of epoetin alfa caused slight increases in pre-implantation loss, post-implantation loss and decreases in the incidence of live fetuses. It is not clear whether these effects reflect a drug effect on the uterine environment or on the conceptus. This animal dose level of 100 Units/kg/day approximates the clinical recommended starting dose, depending on the patient's treatment indication, but may be lower than the clinical dose in patients whose doses have been adjusted.

14 CLINICAL STUDIES

14.1 Patients with Chronic Kidney Disease

Adult Patients on Dialysis

Patients with chronic kidney disease on dialysis: ESA effects on rates of transfusion

In clinical studies of patients with CKD on dialysis, epoetin alfa increased hemoglobin levels and decreased the need for RBC transfusion. Overall, more than 95% of patients were RBC transfusion-independent after receiving epoetin alfa for 3 months. In clinical studies at starting doses of 50 to 150 Units/kg 3 times weekly, adult patients responded with an average rate of hemoglobin rise as presented in Table 8.

Table 8. Average Rate of Hemoglobin Rise in 2 Weeks
Starting Dose (3 Times Weekly Intravenously) | Hemoglobin Increase in 2 Weeks
50 Units/kg | 0.5 g/dL
100 Units/kg | 0.8 g/dL
150 Units/kg | 1.2 g/dL

The safety and efficacy of epoetin alfa were evaluated in 13 clinical studies involving intravenous administration to a total of 1010 patients on dialysis with anemia. Overall, more than 90% of the patients treated with epoetin alfa experienced improvement in hemoglobin concentrations. In the 3 largest of these clinical studies, the median maintenance dose necessary to maintain the hemoglobin between 10 to 12 g/dL was approximately 75 Units/kg 3 times weekly. More than 95% of patients were able to avoid RBC transfusions. In the largest US multicenter study, approximately 65% of the patients received doses of 100 Units/kg 3 times weekly or less to maintain their hemoglobin at approximately 11.7 g/dL. Almost 10% of patients received a dose of 25 Units/kg or less, and approximately 10% received a dose of more than 200 Units/kg 3 times weekly to maintain their hemoglobin at this level.

In the Normal Hematocrit Study, the yearly transfusion rate was 51.5% in the lower hemoglobin group (10 g/dL) and 32.4% in the higher hemoglobin group (14 g/dL).

Other ESA trials

In a 26-week, double-blind, placebo-controlled study, 118 patients on dialysis with an average hemoglobin of approximately 7 g/dL were randomized to either epoetin alfa or placebo. By the end of the study, average hemoglobin increased to approximately 11 g/dL in the epoetin alfa-treated patients and remained unchanged in patients receiving placebo. Epoetin alfa-treated patients experienced improvements in exercise tolerance and patient-reported physical functioning at month 2 that were maintained throughout the study.

A multicenter, unit-dose study was also conducted in 119 patients receiving peritoneal dialysis who self-administered epoetin alfa subcutaneously. Patients responded to epoetin alfa administered subcutaneously in a manner similar to patients receiving intravenous administration.

Pediatric Patients with CKD on Dialysis

The safety and efficacy of epoetin alfa were studied in a placebo-controlled, randomized study of 113 pediatric patients with anemia (hemoglobin ≤ 9 g/dL) undergoing peritoneal dialysis or hemodialysis. The initial dose of epoetin alfa was 50 Units/kg intravenously or subcutaneously 3 times weekly. The dose of study drug was titrated to achieve either a hemoglobin of 10 to 12 g/dL or an absolute increase in hemoglobin of 2 g/dL over baseline.

At the end of the initial 12 weeks, a statistically significant rise in mean hemoglobin (3.1 g/dL vs. 0.3 g/dL) was observed only in the epoetin alfa arm. The proportion of pediatric patients achieving a hemoglobin of 10 g/dL, or an increase in hemoglobin of 2 g/dL over baseline, at any time during the first 12 weeks was higher in the epoetin alfa arm (96% vs. 58%). Within 12 weeks of initiating epoetin alfa therapy, 92.3% of the pediatric patients were RBC transfusion independent as compared to 65.4% who received placebo. Among patients who received 36 weeks of epoetin alfa, hemodialysis patients received a higher median maintenance dose [167 Units/kg/week (n = 28) vs. 76 Units/kg/week (n = 36)] and took longer to achieve a hemoglobin of 10 to 12 g/dL (median time to response 69 days vs. 32 days) than patients undergoing peritoneal dialysis.

Adult Patients with CKD Not Requiring Dialysis

Four clinical studies were conducted in patients with CKD not on dialysis involving 181 patients treated with epoetin alfa. These patients responded to epoetin alfa therapy in a manner similar to that observed in patients on dialysis. Patients with CKD not on dialysis demonstrated a dose-dependent and sustained increase in hemoglobin when epoetin alfa was administered by either an intravenous or subcutaneous route, with similar rates of rise of hemoglobin when epoetin alfa was administered by either route.

Patients with chronic kidney disease not on dialysis: ESA effects on rates of transfusion

In TREAT, a randomized, double-blind trial of 4038 patients with CKD and type 2 diabetes not on dialysis, a post-hoc analysis showed that the proportion of patients receiving RBC transfusions was lower in patients administered an ESA to target a hemoglobin of 13 g/dL compared to the control arm in which an ESA was administered intermittently if hemoglobin concentration decreased to less than 9 g/dL (15% versus 25%, respectively). In CHOIR, a randomized open-label study of 1432 patients with CKD not on dialysis, use of epoetin alfa to target a higher (13.5 g/dL) versus lower (11.3 g/dL) hemoglobin goal did not reduce the use of RBC transfusions. In each trial, no benefits occurred for the cardiovascular or end-stage renal disease outcomes. In each trial, the potential benefit of ESA therapy was offset by worse cardiovascular safety outcomes resulting in an unfavorable benefit-risk profile [see Warnings and Precautions (5.1)].

ESA Effects on rates of death and other serious cardiac adverse reactions

Three randomized outcome trials (Normal Hematocrit Study [NHS], Correction of Anemia with Epoetin Alfa in Chronic Kidney Disease [CHOIR], and Trial of Darbepoetin Alfa in Type 2 Diabetes and CKD [TREAT]) have been conducted in patients with CKD using epoetin alfa/darbepoetin alfa to target higher vs. lower hemoglobin levels. Though these trials were designed to establish a cardiovascular or renal benefit of targeting higher hemoglobin levels, in all 3 studies, patients randomized to the higher hemoglobin target experienced worse cardiovascular outcomes and showed no reduction in progression to ESRD. In each trial, the potential benefit of ESA therapy was offset by worse cardiovascular safety outcomes resulting in an unfavorable benefit-risk profile [see Warnings and Precautions (5.1)].

14.2 Zidovudine-treated Patients with HIV Infection

The safety and efficacy of epoetin alfa were evaluated in 4 placebo-controlled studies enrolling 297 anemic patients (hemoglobin < 10 g/dL) with HIV infection receiving concomitant therapy with zidovudine. In the subgroup of patients (89/125 epoetin alfa and 88/130 placebo) with pre-study endogenous serum erythropoietin levels ≤ 500 mUnits/mL, epoetin alfa reduced the mean cumulative number of units of blood transfused per patient by approximately 40% as compared to the placebo group. Among those patients who required RBC transfusions at baseline, 43% of patients treated with epoetin alfa versus 18% of placebo-treated patients were RBC transfusion-independent during the second and third months of therapy. Epoetin alfa therapy also resulted in significant increases in hemoglobin in comparison to placebo. When examining the results according to the weekly dose of zidovudine received during month 3 of therapy, there was a statistically significant reduction (p < 0.003) in RBC transfusion requirements in patients treated with epoetin alfa (n = 51) compared to placebo-treated patients (n = 54) whose mean weekly zidovudine dose was ≤ 4200 mg/week.

Approximately 17% of the patients with endogenous serum erythropoietin levels ≤ 500 mUnits/mL receiving epoetin alfa in doses from 100 to 200 Units/kg 3 times weekly achieved a hemoglobin of 12.7 g/dL without administration of RBC transfusions or significant reduction in zidovudine dose. In the subgroup of patients whose pre-study endogenous serum erythropoietin levels were > 500 mUnits/mL, epoetin alfa therapy did not reduce RBC transfusion requirements or increase hemoglobin compared to the corresponding responses in placebo-treated patients.

14.3 Patients with Cancer on Chemotherapy

The safety and effectiveness of epoetin alfa was assessed in two multicenter, randomized (1:1), placebo-controlled, double-blind studies (Study C1 and Study C2) and a pooled analysis of six additional randomized (1:1), multicenter, placebo-controlled, double-blind studies. All studies were conducted in patients with anemia due to concomitantly administered cancer chemotherapy. Study C1 enrolled 344 adult patients, Study C2 enrolled 222 pediatric patients, and the pooled analysis contained 131 patients randomized to epoetin alfa or placebo. In Studies C1 and C2, efficacy was demonstrated by a reduction in the proportion of patients who received an RBC transfusion, from week 5 through end of the study, with the last-known RBC transfusion status carried forward for patients who discontinued treatment. In the pooled analysis, efficacy was demonstrated by a reduction in the proportion of patients who received an RBC transfusion from week 5 through end of the study in the subset of patients who were remaining on therapy for 6 or more weeks.

Study C1

Study C1 was conducted in patients with anemia (hemoglobin < 11.5 g/dL for males; < 10.5 g/dL for females) with non-myeloid malignancies receiving myelosuppressive chemotherapy. Randomization was stratified by type of malignancy (lung vs. breast vs. other), concurrent radiation therapy planned (yes or no), and baseline hemoglobin (< 9 g/dL vs. ≥ 9 g/dL); patients were randomized to epoetin alfa 40,000 Units (n = 174) or placebo (n = 170) as a weekly subcutaneous injection commencing on the first day of the chemotherapy cycle.

Ninety-one percent of patients were white, 44% were male, and the median age of patients was 66 years (range: 20 to 88 years). The proportion of patients withdrawn from the study prior to week 5 was less than 10% for placebo-treated or epoetin-treated patients. Per protocol, the last available hemoglobin values from patients who dropped out were included in the efficacy analyses. Efficacy results are shown in Table 9.

Table 9. Study C1: Proportion of Patients Transfused
 | Week 5 Through Week 16 or End of Study [Last-known RBC transfusion status carried forward for patients who discontinued treatment.]
Chemotherapy Regimen | Epoetin alfa (n = 174) | Placebo (n = 170)
All Regimens | 14% (25/174) [Two-sided p < 0.001, logistic regression analysis adjusting for accrual rate and stratification variables.] | 28% (48/170)
Regimens without cisplatin | 14% (21/148) | 26% (35/137)
Regimens containing cisplatin | 15% (4/26) | 39% (13/33)

Study C2

Study C2 was conducted in 222 patients with anemia, ages 5 to 18, receiving chemotherapy for the treatment of various childhood malignancies. Randomization was stratified by cancer type (solid tumors, Hodgkin's disease, acute lymphocytic leukemia, vs. non-Hodgkin's lymphoma); patients were randomized to receive epoetin alfa at 600 Units/kg maximum 40,000 Units (n = 111) or placebo (n = 111) as a weekly intravenous injection.

Sixty-nine percent of patients were white, 55% were male, and the median age of patients was 12 years (range: 5 to 18 years). Two (2%) of placebo-treated patients and 3 (3%) of epoetin alfa-treated patients dropped out of the study prior to week 5. There were fewer RBC transfusions from week 5 through the end-of-study in epoetin alfa-treated patients [51% (57/111)] compared to placebo-treated patients [69% (77/111)]. There was no evidence of an improvement in health-related quality of life, including no evidence of an effect on fatigue, energy, or strength in patients receiving epoetin alfa as compared to those receiving placebo.

Pooled Analysis (Three Times Per Week Dosing)

The results of 6 studies of similar design and that randomized 131 patients to epoetin alfa or placebo were pooled to assess the safety and effectiveness of epoetin alfa. Patients were randomized to receive epoetin alfa at 150 Units/kg (n = 63) or placebo (n = 68), subcutaneously three times per week for 12 weeks in each study. Across all studies, 72 patients were treated with concomitant non cisplatin-containing chemotherapy regimens and 59 patients were treated with concomitant cisplatin-containing chemotherapy regimens. Twelve patients (19%) in the epoetin alfa arm and 10 patients (15%) in the placebo-arm dropped out prior to week 6 and are excluded from efficacy analyses.

Table 10. Proportion of Patients Transfused in the Pooled Analysis for Three Times Per Week Dosing
 | Week 5 Through Week 12 or End of Study [Limited to patients remaining on study beyond week 6 and includes only RBC transfusions during weeks 5–12.]
Chemotherapy Regimen | Epoetin alfa | Placebo
All Regimens | 22% (11/51) [Two-sided p < 0.05, unadjusted.] | 43% (25/58)
Regimens without cisplatin | 21% (6/29) | 33% (11/33)
Regimens containing cisplatin | 23% (5/22) | 56% (14/25)

14.4 Surgery Patients

The safety and efficacy of epoetin alfa were evaluated in a placebo-controlled, double-blind study (S1) enrolling 316 patients scheduled for major, elective orthopedic hip or knee surgery who were expected to require ≥ 2 units of blood and who were not able or willing to participate in an autologous blood donation program. Patients were stratified into 1 of 3 groups based on their pretreatment hemoglobin [≤ 10 g/dL (n = 2), > 10 to ≤ 13 g/dL (n = 96), and > 13 to ≤ 15 g/dL (n = 218)] and then randomly assigned to receive 300 Units/kg epoetin alfa, 100 Units/kg epoetin alfa, or placebo by subcutaneous injection for 10 days before surgery, on the day of surgery, and for 4 days after surgery. All patients received oral iron and a low-dose, postoperative warfarin regimen.

Treatment with epoetin alfa 300 Units/kg significantly (p = 0.024) reduced the risk of allogeneic RBC transfusion in patients with a pretreatment hemoglobin of > 10 to ≤ 13 g/dL; 5/31 (16%) of patients treated with epoetin alfa 300 Units/kg, 6/26 (23%) of patients treated with epoetin alfa 100 Units/kg, and 13/29 (45%) of placebo-treated patients were transfused. There was no significant difference in the number of patients transfused between epoetin alfa (9% 300 Units/kg, 6% 100 Units/kg) and placebo (13%) in the > 13 to ≤ 15 g/dL hemoglobin stratum. There were too few patients in the ≤ 10 g/dL group to determine if epoetin alfa is useful in this hemoglobin strata. In the > 10 to ≤ 13 g/dL pretreatment stratum, the mean number of units transfused per epoetin alfa-treated patient (0.45 units blood for 300 Units/kg, 0.42 units blood for 100 Units/kg) was less than the mean transfused per placebo-treated patient (1.14 units) (overall p = 0.028). In addition, mean hemoglobin, hematocrit, and reticulocyte counts increased significantly during the presurgery period in patients treated with epoetin alfa.

Epoetin alfa was also evaluated in an open-label, parallel-group study (S2) enrolling 145 patients with a pretreatment hemoglobin level of ≥ 10 to ≤ 13 g/dL who were scheduled for major orthopedic hip or knee surgery and who were not participating in an autologous program. Patients were randomly assigned to receive 1 of 2 subcutaneous dosing regimens of epoetin alfa (600 Units/kg once weekly for 3 weeks prior to surgery and on the day of surgery, or 300 Units/kg once daily for 10 days prior to surgery, on the day of surgery, and for 4 days after surgery). All patients received oral iron and appropriate pharmacologic anticoagulation therapy.

From pretreatment to presurgery, the mean increase in hemoglobin in the 600 Units/kg weekly group (1.44 g/dL) was greater than that observed in the 300 Units/kg daily group. The mean increase in absolute reticulocyte count was smaller in the weekly group (0.11 × 10^6/mm^3) compared to the daily group (0.17 × 10^6/mm^3). Mean hemoglobin levels were similar for the 2 treatment groups throughout the postsurgical period.

The erythropoietic response observed in both treatment groups resulted in similar RBC transfusion rates [11/69 (16%) in the 600 Units/kg weekly group and 14/71 (20%) in the 300 Units/kg daily group]. The mean number of units transfused per patient was approximately 0.3 units in both treatment groups.

16 HOW SUPPLIED/STORAGE AND HANDLING

RETACRIT (epoetin alfa-epbx) injection is a sterile, clear, and colorless solution in single-dose and multiple-dose vials available as:

Unit of Sale | Strength | Each Single Unit of Use
NDC 59353-002-10 Carton containing 10 vials | 2,000 Units/mL | NDC 59353-002-01 1 mL Single-dose vial
NDC 59353-003-10 Carton containing 10 vials | 3,000 Units/mL | NDC 59353-003-01 1 mL Single-dose vial
NDC 59353-004-10 Carton containing 10 vials | 4,000 Units/mL | NDC 59353-004-01 1 mL Single-dose vial
NDC 59353-010-10 Carton containing 10 vials | 10,000 Units/mL | NDC 59353-010-01 1 mL Single-dose vial
NDC 59353-120-10 Carton containing 10 vials with a freeze strip indicator | 20,000 Units/mL | NDC 59353-120-01 1 mL Multiple-dose vial
NDC 59353-220-10 Carton containing 10 vials with a freeze strip indicator | 20,000 Units/ 2 mL (10,000 Units/mL) | NDC 59353-220-01 2 mL Multiple-dose vial

STORAGE AND HANDLING

Store refrigerated at 2°C to 8°C (36°F to 46°F). Do not freeze. When exposed to freezing temperatures, the green area of the freeze strip indicator in the carton of the multiple-dose vials will show signs of cloudy or white discoloration.

Do not shake. Do not use RETACRIT that has been shaken or frozen or if the green area of the freeze strip indicator is cloudy or white.

Store RETACRIT vials in the original carton until use to protect from light.

The vial stopper used for RETACRIT is not made with natural rubber latex.

17 PATIENT COUNSELING INFORMATION

Advise the patient to read the FDA-approved patient labeling (Medication Guide and Instructions for Use).

Inform patients:

- Of the increased risks of mortality, serious cardiovascular reactions, thromboembolic reactions, stroke, and tumor progression [see Warnings and Precautions (5.1, 5.2)].
- To undergo regular blood pressure monitoring, adhere to prescribed anti-hypertensive regimen and follow recommended dietary restrictions.
- To contact their healthcare provider for new-onset neurologic symptoms or change in seizure frequency.
- Of the need to have regular laboratory tests for hemoglobin.
- Risks are associated with benzyl alcohol in neonates, infants, pregnant women, and lactating women [see Use in Specific Populations (8.1, 8.2, 8.4)].

Instruct patients who self-administer RETACRIT of the:

- Importance of following the Instructions for Use.
- Dangers of reusing needles, syringes, or unused portions of single-dose vials.
- Proper disposal of used syringes, needles, and unused vials, and of the full container.

This product's labeling may have been updated. For the most recent prescribing information, please visit www.pfizer.com.

Manufactured by Hospira, Inc., a Pfizer Company, Lake Forest, IL 60045 USA
US License No. 1974

Distributed by Vifor (International) Inc., Rechenstrasse 37, 9014 St. Gallen, Switzerland

LAB-1280-8.0

MEDICATION GUIDE
RETACRIT® (Ret-uh-krit)
(epoetin alfa-epbx)

Read this Medication Guide:

- before you start RETACRIT.
- if you are told by your healthcare provider that there is new information about RETACRIT.
- if you are told by your healthcare provider that you may inject RETACRIT at home, read this Medication Guide each time you receive a new supply of medicine.

This Medication Guide does not take the place of talking to your healthcare provider about your medical condition or your treatment. Talk with your healthcare provider regularly about the use of RETACRIT and ask if there is new information about RETACRIT.

What is the most important information I should know about RETACRIT?

RETACRIT may cause serious side effects that can lead to death, including:

For people with cancer:

- Your tumor may grow faster and you may die sooner if you choose to take RETACRIT. Your healthcare provider will talk with you about these risks.

For all people who take RETACRIT, including people with cancer or chronic kidney disease:

- Serious heart problems, such as heart attack or heart failure, and stroke. You may die sooner if you are treated with RETACRIT to increase red blood cells (RBCs) to near the same level found in healthy people.
- Blood clots. Blood clots may happen at any time while taking RETACRIT. If you are receiving RETACRIT for any reason and you are going to have surgery, talk to your healthcare provider about whether or not you need to take a blood thinner to lessen the chance of blood clots during or following surgery. Blood clots can form in blood vessels (veins), especially in your leg (deep venous thrombosis or DVT). Pieces of a blood clot may travel to the lungs and block the blood circulation in the lungs (pulmonary embolus).
- Call your healthcare provider or get medical help right away if you have any of these symptoms:
  - Chest pain
  - Trouble breathing or shortness of breath
  - Pain in your legs, with or without swelling
  - A cool or pale arm or leg
  - Sudden confusion, trouble speaking, or trouble understanding others' speech
  - Sudden numbness or weakness in your face, arm, or leg, especially on one side of your body
  - Sudden trouble seeing
  - Sudden trouble walking, dizziness, loss of balance or coordination
  - Loss of consciousness (fainting)
  - Hemodialysis vascular access stops working

See "What are the possible side effects of RETACRIT?" below for more information.

If you decide to take RETACRIT, your healthcare provider should prescribe the smallest dose of RETACRIT that is necessary to reduce your chance of needing RBC transfusions.

What is RETACRIT?

RETACRIT is a prescription medicine used to treat anemia. People with anemia have a lower-than-normal number of RBCs. RETACRIT works like the human protein called erythropoietin to help your body make more RBCs. RETACRIT is used to reduce or avoid the need for RBC transfusions.

RETACRIT may be used to treat anemia if it is caused by:

- Chronic kidney disease (you may or may not be on dialysis).
- Chemotherapy that will be used for at least two months after starting RETACRIT.
- A medicine called zidovudine (AZT) used to treat HIV infection.

RETACRIT may also be used to reduce the chance you will need RBC transfusions if you are scheduled for certain surgeries where a lot of blood loss is expected.

If your hemoglobin level stays too high or if your hemoglobin goes up too quickly, this may lead to serious health problems which may result in death. These serious health problems may happen if you take RETACRIT, even if you do not have an increase in your hemoglobin level.

RETACRIT has not been proven to improve quality of life, fatigue, or well-being.

RETACRIT should not be used for treatment of anemia:

- If you have cancer and you will not be receiving chemotherapy that may cause anemia.
- If you have a cancer that has a high chance of being cured. Talk with your healthcare provider about the kind of cancer you have.
- If your anemia caused by chemotherapy treatment can be managed by RBC transfusion.
- In place of emergency treatment for anemia (RBC transfusions).

RETACRIT should not be used to reduce the chance you will need RBC transfusions if:

- You are scheduled for surgery on your heart or blood vessels.
- You are able and willing to donate blood prior to surgery.

It is not known if RETACRIT is safe and effective in treating anemia in children less than 1 month old who have chronic kidney disease and in children less than 5 years old who have anemia caused by chemotherapy.

Who should not take RETACRIT?

Do not take RETACRIT if you:

- Have cancer and have not been counseled by your healthcare provider about treatment with RETACRIT.
- Have high blood pressure that is not controlled (uncontrolled hypertension).
- Have been told by your healthcare provider that you have or have ever had a type of anemia called Pure Red Cell Aplasia (PRCA) that starts after treatment with RETACRIT or other erythropoietin protein medicines.
- Have had a serious allergic reaction to RETACRIT or other epoetin alfa products.

Do not give RETACRIT from multiple-dose vials to:

- Pregnant or breastfeeding women
- Babies

Before taking RETACRIT, tell your healthcare provider about all of your medical conditions, including if you:

- Have heart disease.
- Have high blood pressure.
- Have had a seizure (convulsion) or stroke.
- Have phenylketonuria. RETACRIT contains phenylalanine (a component of aspartame).
- Receive dialysis treatment.
- Are pregnant or plan to become pregnant. It is not known if RETACRIT may harm your unborn baby. Talk to your healthcare provider about possible pregnancy and birth control choices that are right for you.
- Are breastfeeding or plan to breastfeed. It is not known if RETACRIT passes into breast milk.

Tell your healthcare provider about all the medicines you take, including prescription and over-the-counter medicines, vitamins, and herbal supplements.

How should I take RETACRIT?

- If you or your caregiver has been trained to give RETACRIT shots (injections) at home:
  - Be sure that you read, understand, and follow the "Instructions for Use" that come with RETACRIT.
  - Take RETACRIT exactly as your healthcare provider tells you to. Do not change the dose of RETACRIT unless told to do so by your healthcare provider.
  - Your healthcare provider will show you how much RETACRIT to use, how to inject it, how often it should be injected, and how to safely throw away the used vials, syringes, and needles.
  - If you miss a dose of RETACRIT, call your healthcare provider right away and ask what to do.
  - If you take more than the prescribed dose of RETACRIT, call your healthcare provider right away.
- During treatment with RETACRIT, continue to follow your healthcare provider's instructions for diet and medicines.
- Have your blood pressure checked as instructed by your healthcare provider.

What are the possible side effects of RETACRIT?

RETACRIT may cause serious side effects, including:

- See "What is the most important information I should know about RETACRIT?"
- High blood pressure. High blood pressure is a common side effect of RETACRIT in people with chronic kidney disease. Your blood pressure may go up or be difficult to control with blood pressure medicine while taking RETACRIT. This can happen even if you have never had high blood pressure before. Your healthcare provider should check your blood pressure often. If your blood pressure does go up, your healthcare provider may prescribe new or more blood pressure medicine.
- Seizures. If you have any seizures while taking RETACRIT, get medical help right away and tell your healthcare provider.
- Antibodies to RETACRIT. Your body may make antibodies to RETACRIT. These antibodies can block or lessen your body's ability to make RBCs and cause you to have severe anemia. Call your healthcare provider if you have unusual tiredness, lack of energy, dizziness, or fainting. You may need to stop taking RETACRIT.
- Serious allergic reactions. Serious allergic reactions can cause a skin rash, itching, shortness of breath, wheezing, dizziness and fainting because of a drop in blood pressure, swelling around your mouth or eyes, fast pulse, or sweating. If you have a serious allergic reaction, stop using RETACRIT and call your healthcare provider or get medical help right away.
- Severe skin reactions. Signs and symptoms of severe skin reactions with RETACRIT may include: skin rash with itching, blisters, skin sores, peeling, or areas of skin coming off. If you have any signs or symptoms of a severe skin reaction, stop using RETACRIT and call your healthcare provider or get medical help right away.
- Dangers of using RETACRIT from multiple-dose vials in newborns, infants, and pregnant or breastfeeding women. Do not use RETACRIT from multiple-dose vials in newborns, infants, pregnant or breastfeeding women because the RETACRIT in these vials contains benzyl alcohol. Benzyl alcohol has been shown to cause brain damage, other serious side effects, and death in newborn and premature babies. If you use RETACRIT from multiple-dose vials you should not breastfeed for at least 2 weeks after the last dose. RETACRIT that comes in single-dose vials does not contain benzyl alcohol. See "Who should not take RETACRIT?"

Common side effects of RETACRIT include:

- joint, muscle, or bone pain
- fever
- cough
- dizziness
- high blood sugar
- low potassium levels in the blood
- chills

- rash
- nausea
- vomiting
- blood vessel blockage
- low white blood cells
- trouble sleeping
- difficulty swallowing

- soreness of mouth
- itching
- headache
- respiratory infection
- weight decrease
- depression
- muscle spasm

- redness and pain at the RETACRIT injection site

These are not all of the possible side effects of RETACRIT. Your healthcare provider can give you a more complete list. Tell your healthcare provider about any side effects that bother you or that do not go away.

Call your doctor for medical advice about side effects. You may report side effects to FDA at 1-800-FDA-1088.

How should I store RETACRIT?

- Do not shake RETACRIT.
- Store RETACRIT vials in the carton it comes in to protect from light.
- Store RETACRIT in the refrigerator between 36°F to 46°F (2°C to 8°C).
- Do not freeze RETACRIT. Do not use the carton of RETACRIT multiple-dose vials if it that has been frozen or if the green area on the freeze strip indicator inside the RETACRIT carton looks white or cloudy.
- Throw away multiple-dose vials of RETACRIT no later than 21 days from the first day that you put a needle into the vial.
- Single-dose vials of RETACRIT should be used only one time. Throw the vial away after use even if there is medicine left in the vial.

Keep RETACRIT and all medicines out of the reach of children.

General information about the safe and effective use of RETACRIT.

Medicines are sometimes prescribed for purposes other than those listed in a Medication Guide. Do not use RETACRIT for a condition for which it was not prescribed. Do not give RETACRIT to other people even if they have the same symptoms that you have. It may harm them. You can ask your healthcare provider or pharmacist for information about RETACRIT that is written for healthcare professionals.

What are the ingredients in RETACRIT?

Active Ingredient: epoetin alfa-epbx

Inactive Ingredients:

- Multiple-dose vials contain benzyl alcohol.
- All single-dose vials contain calcium chloride dehydrate, glycine, isoleucine, leucine, L-glutamic acid, phenylalanine, polysorbate 20, sodium chloride, sodium phosphate dibasic anhydrous, sodium phosphate monobasic monohydrate, and threonine, in water for injection. Sodium hydroxide and hydrochloric acid may be added to adjust the pH.
- All multiple-dose vials contain benzyl alcohol, L-methionine, polysorbate 20, sodium phosphate dibasic anhydrous, sodium phosphate monobasic monohydrate, and sucrose, in water for injection. Sodium hydroxide and hydrochloric acid may be added to adjust the pH.

Manufactured by Hospira, Inc., a Pfizer Company, Lake Forest, IL 60045 USA
US License No. 1974
Distributed by Vifor (International) Inc., Rechenstrasse 37, 9014 St. Gallen, Switzerland

LAB-1281-7.0
For more information, go to www.pfizer.com or call 1-800-438-1985.

This Medication Guide has been approved by the U.S. Food and Drug Administration. Revised: 6/2024

Instructions for Use

RETACRIT® (Ret-uh-krit)
(epoetin alfa-epbx)

Use these Instructions for Use if you or your caregiver has been trained to give RETACRIT injections at home. Do not give yourself the injection unless you have received training from your healthcare provider. If you are not sure about giving the injection or you have questions, ask your healthcare provider for help.

Before reading these Instructions for Use, read the Medication Guide that comes with RETACRIT for the most important information you need to know.

When you receive your RETACRIT vial make sure that:

- The name RETACRIT appears on the carton and vial label.
- The expiration date on the vial label has not passed. Do not use a vial of RETACRIT after the expiration date on the label.
- The dose strength of the RETACRIT vial (number of Units per mL on the vial label) is the same as your healthcare provider prescribed.
- You understand what the dose strength of RETACRIT means. RETACRIT vials come in several dose strengths. For example, the dose strength may be described as 10,000 Units/mL on the vial label. This strength means that 10,000 Units of medicine are contained in each 1 mL (milliliter) of liquid. Your healthcare provider may also refer to a mL as a "cc." One mL is the same as one "cc."
- The RETACRIT liquid in the vial is clear and colorless. Do not use RETACRIT if the liquid in the vial looks discolored or cloudy, or if the liquid has lumps, flakes, or particles.
- The RETACRIT vial has a color cap on the top of the vial. Do not use a vial of RETACRIT if the color cap on the top of the vial has been removed or is missing.
- Use only the type of disposable syringe and needle that your healthcare provider has prescribed.
- Do not shake RETACRIT. Shaking could cause RETACRIT not to work. If you shake RETACRIT, the solution in the vial may look foamy and should not be used.
- Do not freeze RETACRIT. Do not use a vial of RETACRIT that has been frozen.
- Do not use the carton of RETACRIT multiple-dose vials if it has been frozen or if the green area on the freeze strip indicator inside the RETACRIT carton looks white or cloudy.
- Store RETACRIT in the refrigerator between 36°F to 46°F (2°C to 8°C).
- Keep RETACRIT away from light.
- Single-dose vials of RETACRIT should be used only one time. Throw the vial away after use even if there is medicine left in the vial.
- After removing a dose from the multiple-dose vial, store the vial in the refrigerator (but not the freezer). Do not store the vial for more than 21 days.
- Throw away the multiple-dose vials as directed by your healthcare provider:
  - if there is not enough medicine left in the multiple-dose vial for another dose, or
  - if it has been more than 21 days since you first put a needle into the multiple-dose vial

How should I prepare for an injection of RETACRIT?

- Always keep an extra syringe and needle on hand.
- Follow your healthcare provider's instructions on how to measure your dose of RETACRIT. This dose will be measured in Units per mL or cc (1 mL is the same as 1 cc). Use a syringe that is marked in tenths of mL (for example, 0.2 mL or 0.2 cc). Using the wrong syringe can lead to a mistake in your dose and you could inject too much or too little RETACRIT.

Only use disposable syringes and needles. Use the syringes and needles only one time and then throw them away as instructed by your healthcare provider.

What do I need to know about the different types of RETACRIT vials?

RETACRIT comes in two different types of vials:

- Single-dose vials
- Multiple-dose vials

The multiple-dose vial of RETACRIT contains the preservative benzyl alcohol. Benzyl alcohol has been shown to cause brain damage, other serious side effects and death in newborn and premature babies. RETACRIT that comes in single-dose vials does not contain benzyl alcohol.

Important: Follow these instructions exactly to help avoid infections.

Preparing the dose:

1. Remove the vial of RETACRIT from the refrigerator. During this time, protect the solution from light.
2. Do not use a single-dose vial of RETACRIT more than one time.
3. Do not shake RETACRIT.
4. Gather the other supplies you will need for your injection (vial, syringe, alcohol wipes, cotton ball, and a puncture-proof container for throwing away the syringe and needle). See Figure 1.

Figure 1

5. Check the date on the RETACRIT vial to be sure that the drug has not expired.
6. Wash your hands well with soap and water before preparing the medicine. See Figure 2.

Figure 2

7. Flip off the protective color cap on the top of the vial. Do not remove the grey rubber stopper. Wipe the top of the grey rubber stopper with an alcohol wipe. See Figures 3 and 4.

Figure 3

Figure 4

8. Check the package containing the syringe. If the package has been opened or damaged, do not use that syringe. Throw away the syringe in the puncture-proof disposable container. If the syringe package is undamaged, open the package and remove the syringe.
9. Using a syringe and needle that has been recommended by your healthcare provider, carefully remove the needle cover. See Figure 5. Then draw air into the syringe by pulling back on the plunger. The amount of air drawn into the syringe should be equal to the amount (mL or cc) of the RETACRIT dose prescribed by your healthcare provider. See Figure 6.

Figure 5

Figure 6

10. With the vial on a flat work surface, insert the needle straight down through the grey rubber stopper of the RETACRIT vial. See Figure 7.
11. Push the plunger of the syringe down to inject the air from the syringe into the vial of RETACRIT. The air injected into the vial will allow RETACRIT to be easily withdrawn into the syringe. See Figure 7.

Figure 7

12. Keep the needle inside the vial. Turn the vial and syringe upside down. Be sure the tip of the needle is in the RETACRIT liquid. Keep the vial upside down. Slowly pull back on the plunger to fill the syringe with RETACRIT liquid to the number (mL or cc) that matches the dose your healthcare provider prescribed. See Figure 8.

Figure 8

13. Keep the needle in the vial. Check for air bubbles in the syringe. A small amount of air is harmless. Too large an air bubble will give you the wrong RETACRIT dose. To remove air bubbles, gently tap the syringe with your fingers until the air bubbles rise to the top of the syringe. Slowly push the plunger up to force the air bubbles out of the syringe. Keep the tip of the needle in the RETACRIT liquid. Pull the plunger back to the number on the syringe that matches your dose. Check again for air bubbles. If there are still air bubbles, repeat the steps above to remove them. See Figures 9 and 10.

Figure 9

Figure 10

14. Double-check that you have the correct dose in the syringe. Lay the vial down on its side with the needle still in it until after you have selected and prepared your site for injection.

Selecting and preparing the injection site:

RETACRIT can be injected into your body using two different ways (routes) as described below. Follow your healthcare provider's instructions about how you should inject RETACRIT. In patients on hemodialysis, the intravenous (IV) route is recommended.

1. Subcutaneous Route:
  1. RETACRIT can be injected directly into a layer of fat under your skin. This is called a subcutaneous injection. When giving subcutaneous injections, follow your healthcare provider's instructions about changing the site for each injection. You may wish to write down the site where you have injected.
  2. Do not inject RETACRIT into an area that is tender, red, bruised, hard, or has scars or stretch marks. Recommended sites for injection are shown in Figure 11 below, including:
    - The outer area of the upper arms
    - The abdomen (except for the 2-inch area around the navel)
    - The front of the middle thighs
    - The upper outer area of the buttocks

Figure 11

  - Clean the skin with an alcohol wipe where the injection is to be made. Be careful not to touch the skin that has been wiped clean. See Figure 12.

Figure 12

  - Double-check that the correct amount of RETACRIT is in the syringe.
  - Remove the prepared syringe and needle from the vial of RETACRIT and hold it in the hand that you will use to inject the medicine.
  - Use the other hand to pinch a fold of skin at the cleaned injection site. Do not touch the cleaned area of skin. See Figure 13.

Figure 13

  - Hold the syringe like you would hold a pencil. Use a quick "dart-like" motion to insert the needle either straight up and down (90-degree angle) or at a slight angle (45 degrees) into the skin. Inject the prescribed dose subcutaneously as directed by your doctor, nurse or pharmacist. See Figure 14.

Figure 14

  - Pull the needle out of the skin and press a cotton ball or gauze over the injection site and hold it there for several seconds. Do not recap the needle.
  - Dispose of the used syringe and needle as described below. Do not reuse syringes and needles.
2. Intravenous Route:
  1. RETACRIT can be injected in your vein through a special access port placed by your healthcare provider. This type of RETACRIT injection is called an intravenous (IV) injection. This route is usually for hemodialysis patients.
  2. If you have a dialysis vascular access, make sure it is working by checking it as your healthcare provider has shown you. Be sure to let your healthcare provider know right away if you are having any problems, or if you have any questions.
  3. Wipe off the venous port of the hemodialysis tubing with an alcohol wipe. See Figure 15.

Figure 15

  - Insert the needle of the syringe into the cleaned venous port and push the plunger all the way down to inject all the RETACRIT. See Figure 16.

Figure 16

  - Remove the syringe from the venous port. Do not recap the needle.
  - Dispose of the used syringe and needle as described below.

How should I dispose of the vials, syringes, and needles?

Do not reuse the single-dose vials, syringes, or needles. Throw away the vials, syringes, and needles as instructed by your healthcare provider or by following these steps:

- Do not throw the vials, syringes, or needles in the household trash or recycle.
- Do not put the needle cover back on the needle.
- Place all used needles and syringes in a puncture-proof disposable container with a lid. Do not use glass or clear plastic containers, or any container that will be recycled or returned to a store.
- Keep the puncture-proof disposable container out of the reach of children.
- When the puncture-proof disposable container is full, tape around the cap or lid to make sure the cap or lid does not come off. Throw away the puncture-proof disposable container as instructed by your healthcare provider. There may be special state and local laws for disposing of used needles and syringes. Do not throw the puncture-proof disposable container in the household trash. Do not recycle.

Keep RETACRIT and all medicines out of reach of children.

These Instructions for Use have been approved by the U.S. Food and Drug Administration.

Manufactured by Hospira, Inc., a Pfizer Company, Lake Forest, IL 60045 USA
US License No. 1974

Distributed by Vifor (International) Inc., Rechenstrasse 37, 9014 St. Gallen, Switzerland

LAB-1282-5.0
Revised: 6/2024

PRINCIPAL DISPLAY PANEL - 2,000 Units/mL Vial Label

NDC 59353-002-01
Rx only

Retacrit®
Epoetin Alfa-epbx
recombinant

2,000 Units/mL

1 mL single-dose vial

CSL Vifor

PRINCIPAL DISPLAY PANEL - 2,000 Units/mL Vial Carton

ALWAYS DISPENSE ENCLOSED MEDICATION GUIDE TO EACH PATIENT
10 x 2,000 Units/mL single-dose vials (containing 1 mL)
NDC 59353-002-10

Retacrit®
Epoetin Alfa-epbx
recombinant

2,000 Units/mL

Phenylketonurics: Contains Phenylalanine, 0.5 mg per mL
For Intravenous or Subcutaneous Use Only
Single-dose vial
Discard unused portion

Rx Only

PRINCIPAL DISPLAY PANEL - 3,000 Units/mL Vial Label

NDC 59353-003-01
Rx only

Retacrit®
Epoetin Alfa-epbx
recombinant

3,000 Units/mL

1 mL single-dose vial

CSL Vifor

PRINCIPAL DISPLAY PANEL - 3,000 Units/mL Vial Carton

ALWAYS DISPENSE ENCLOSED MEDICATION GUIDE TO EACH PATIENT
10 x 3,000 Units/mL single-dose vials (containing 1 mL)
NDC 59353-003-10

Retacrit®
Epoetin Alfa-epbx
recombinant

3,000 Units/mL

Phenylketonurics: Contains Phenylalanine, 0.5 mg per mL
For Intravenous or Subcutaneous Use Only
Single-dose vial
Discard unused portion

Rx Only

PRINCIPAL DISPLAY PANEL - 4,000 Units/mL Vial Label

NDC 59353-004-01
Rx only

Retacrit®
Epoetin Alfa-epbx
recombinant

4,000 Units/mL

1 mL single-dose vial

CSL Vifor

PRINCIPAL DISPLAY PANEL - 4,000 Units/mL Vial Carton

ALWAYS DISPENSE ENCLOSED MEDICATION GUIDE TO EACH PATIENT
10 x 4,000 Units/mL single-dose vials (containing 1 mL)
NDC 59353-004-10

Retacrit®
Epoetin Alfa-epbx
recombinant

4,000 Units/mL

Phenylketonurics: Contains Phenylalanine, 0.5 mg per mL
For Intravenous or Subcutaneous Use Only
Single-dose vial
Discard unused portion

Rx Only

PRINCIPAL DISPLAY PANEL - 10,000 Units/mL Vial Label

NDC 59353-010-01
Rx only

Retacrit®
Epoetin Alfa-epbx
recombinant

10,000 Units/mL

1 mL single-dose vial

CSL Vifor

PRINCIPAL DISPLAY PANEL - 10,000 Units/mL Vial Carton

ALWAYS DISPENSE ENCLOSED MEDICATION GUIDE TO EACH PATIENT
10 x 10,000 Units/mL single-dose vials (containing 1 mL)
NDC 59353-010-10

Retacrit®
Epoetin Alfa-epbx
recombinant

10,000 Units/mL

Phenylketonurics: Contains Phenylalanine, 0.5 mg per mL
For Intravenous or Subcutaneous Use Only
Single-dose vial
Discard unused portion

Rx Only

PRINCIPAL DISPLAY PANEL - 20,000 Units/mL Vial Label

NDC 59353-120-01
Rx only

Retacrit®
Epoetin Alfa-epbx
recombinant

20,000 Units/mL

1 mL Multiple-Dose Vial

CSL Vifor

PRINCIPAL DISPLAY PANEL - 20,000 Units/mL Vial Carton

ALWAYS DISPENSE ENCLOSED MEDICATION GUIDE TO EACH PATIENT
10 x 20,000 Units/mL multiple-dose vials (containing 1 mL)
NDC 59353-120-10

Retacrit®
Epoetin Alfa-epbx
recombinant

20,000 Units/mL

For Intravenous or Subcutaneous Use Only
Sterile Solution - Preserved
Multiple-Dose Vials

Rx only

PRINCIPAL DISPLAY PANEL - 20,000 Units/2 mL Vial Label

NDC 59353-220-01
Rx only

Retacrit®
Epoetin Alfa-epbx
recombinant

20,000 Units/2 mL
(10,000 Units/mL)

2 mL Multiple-Dose Vial

CSL Vifor

PRINCIPAL DISPLAY PANEL - 20,000 Units/2 mL Vial Carton

ALWAYS DISPENSE ENCLOSED MEDICATION GUIDE TO EACH PATIENT
NDC 59353-220-10
10 x 20,000 Units/2 mL (10,000 Units/mL) multiple-dose vials (containing 2 mL)

Retacrit®
Epoetin Alfa-epbx
recombinant

20,000 Units/2 mL (10,000 Units/mL)

For Intravenous or Subcutaneous Use Only
Sterile Solution - Preserved
Multiple-Dose Vials

Rx only